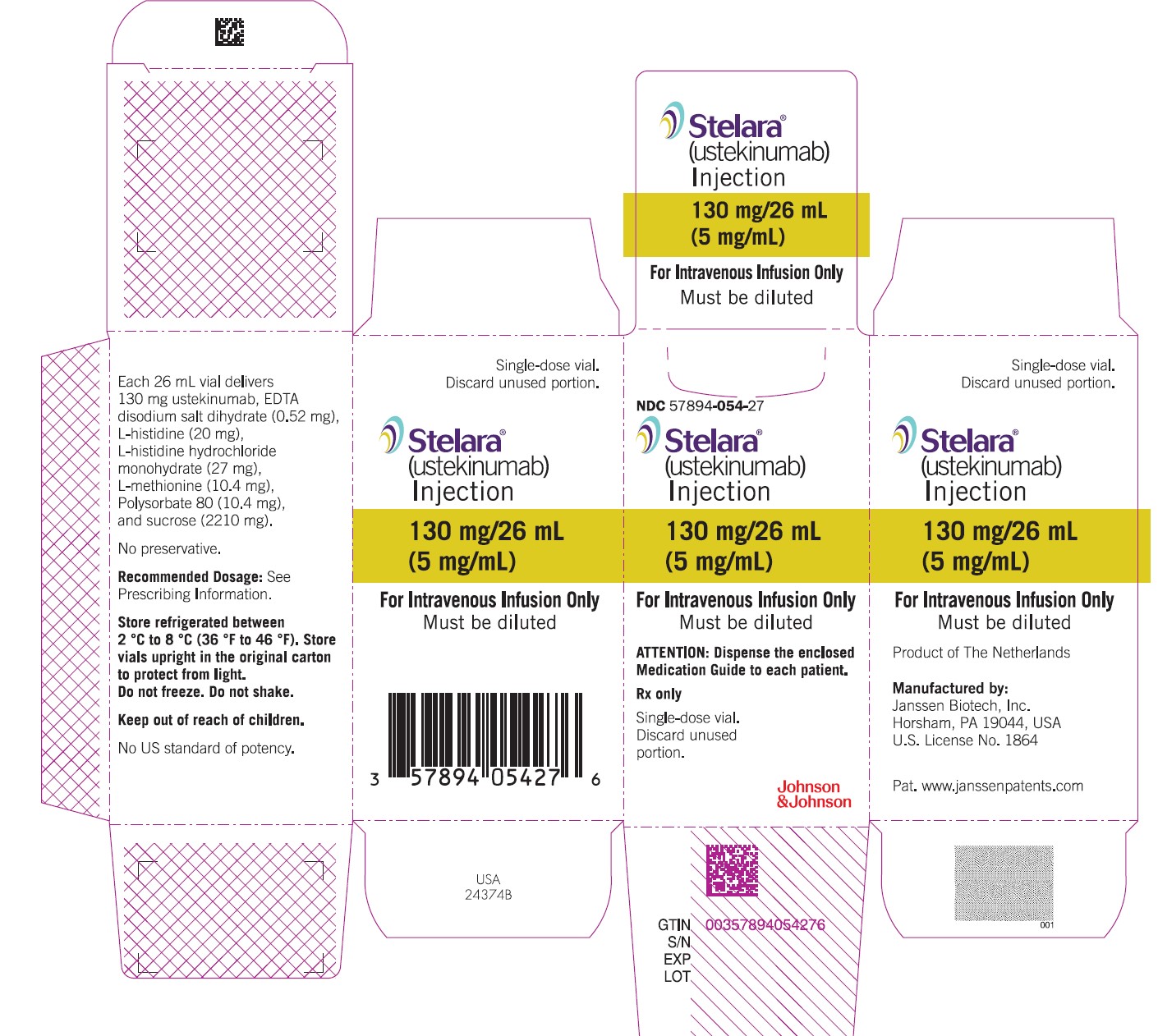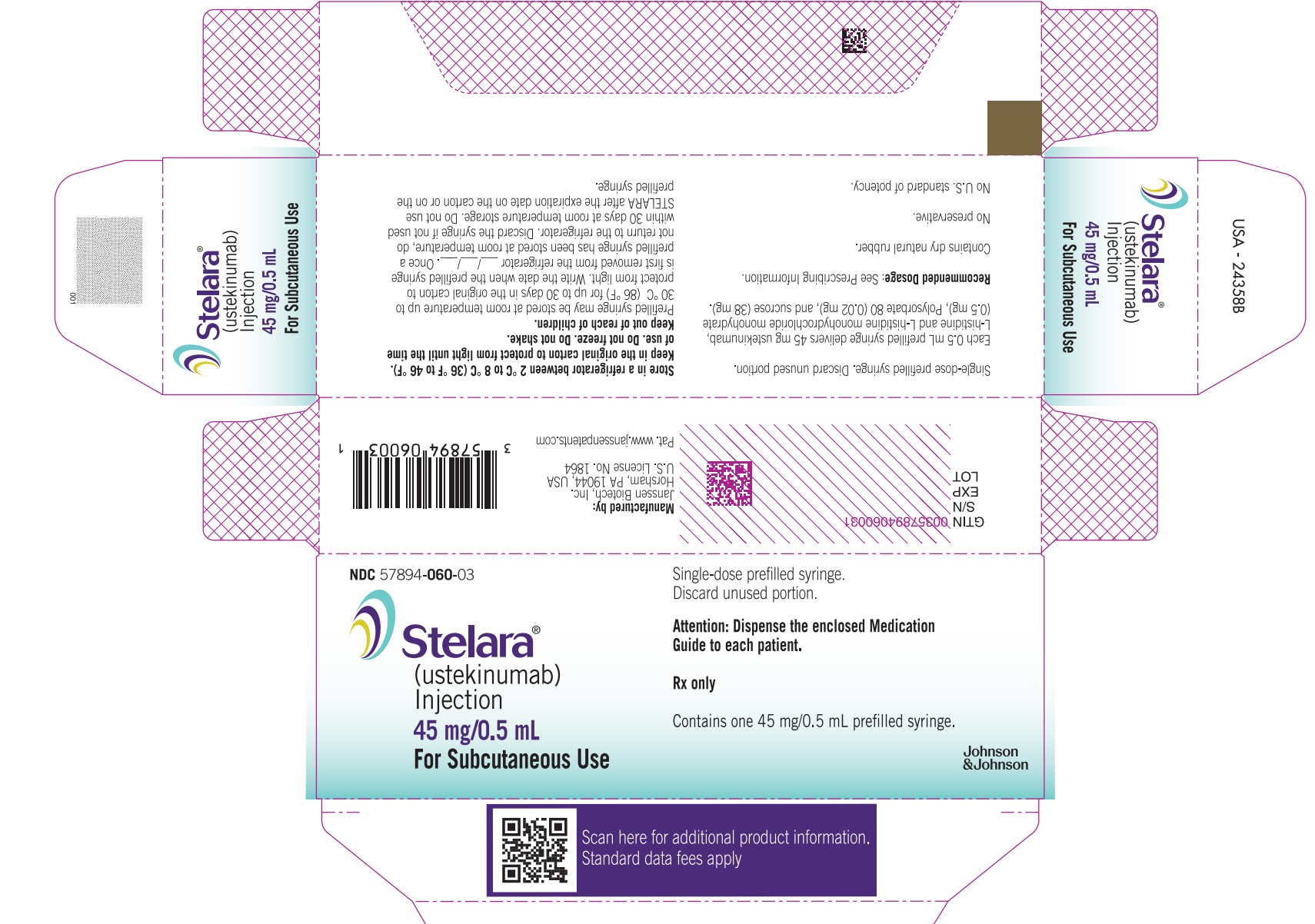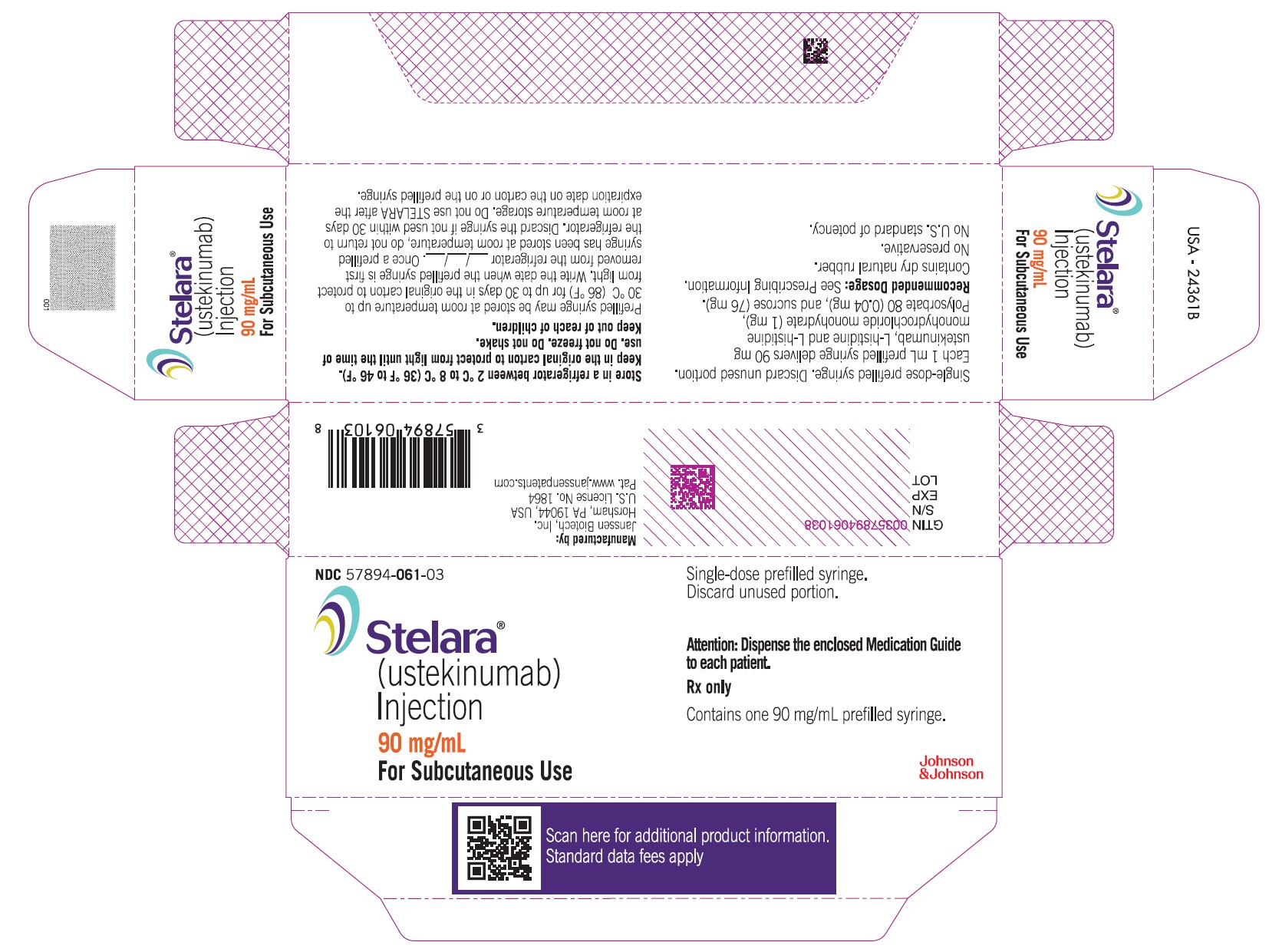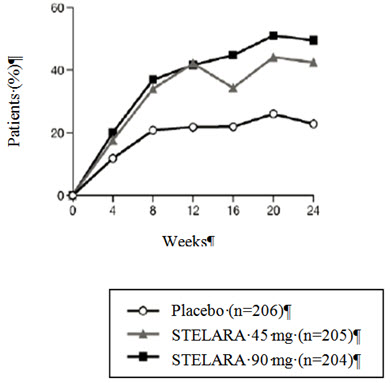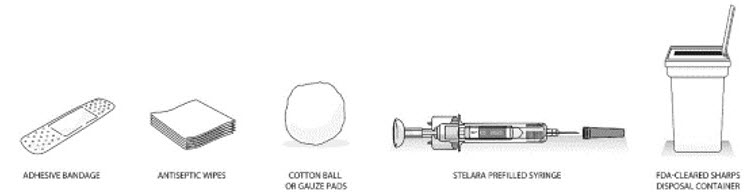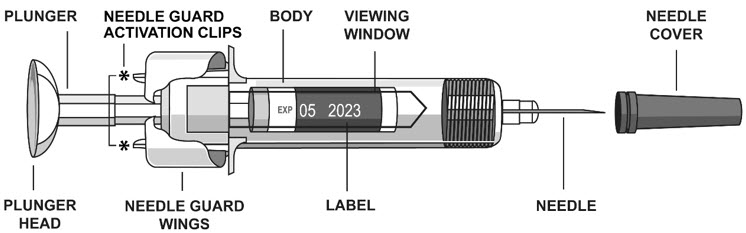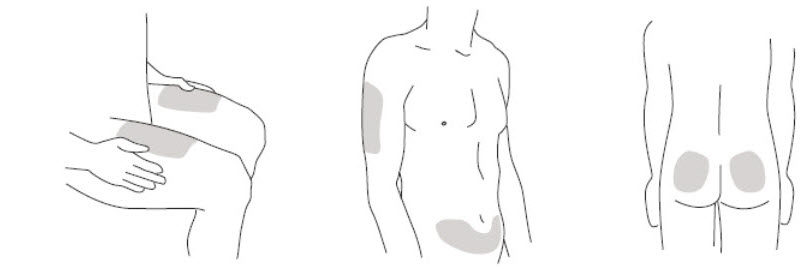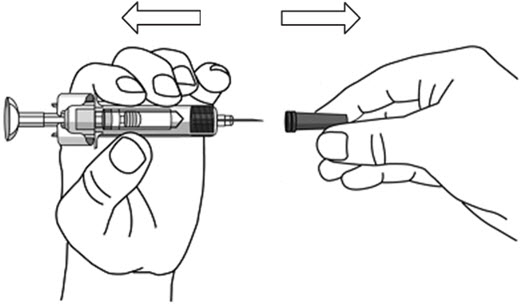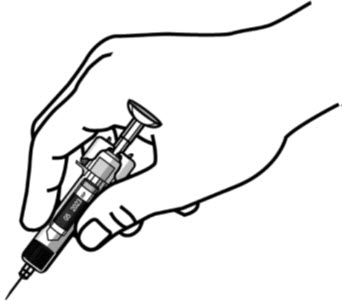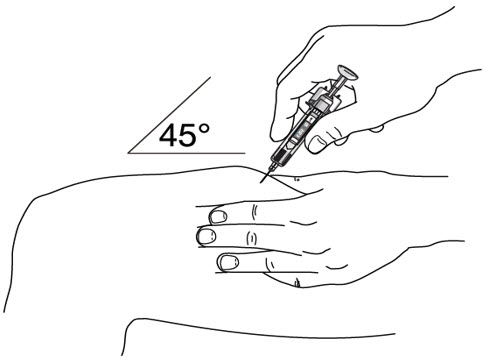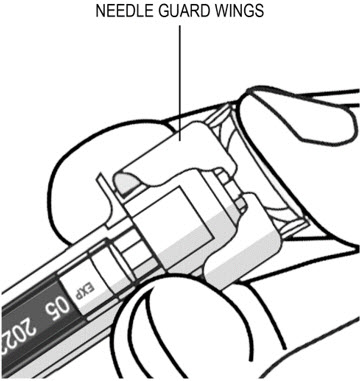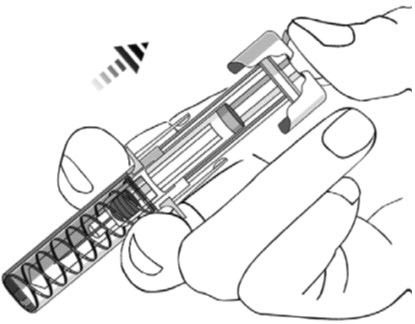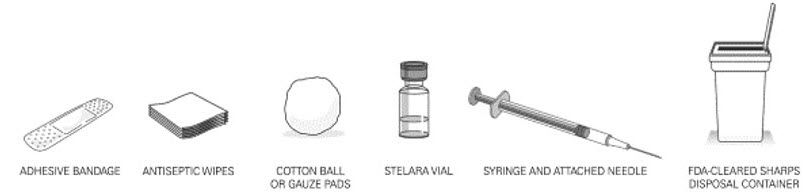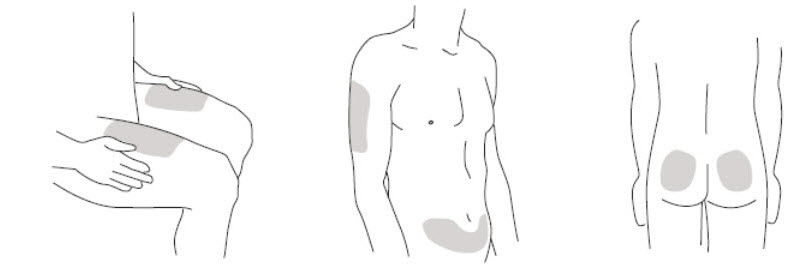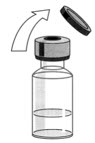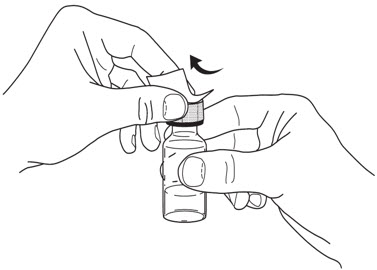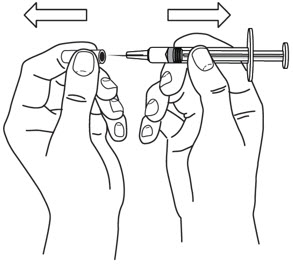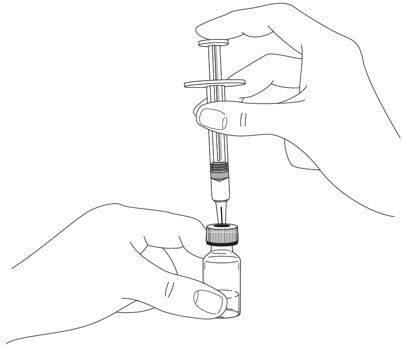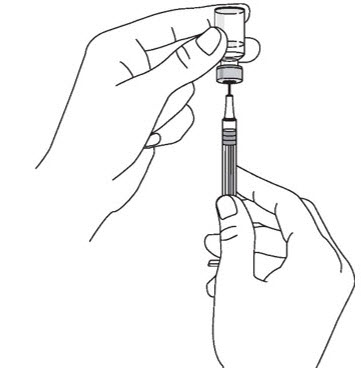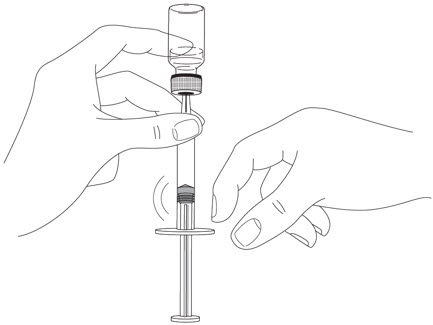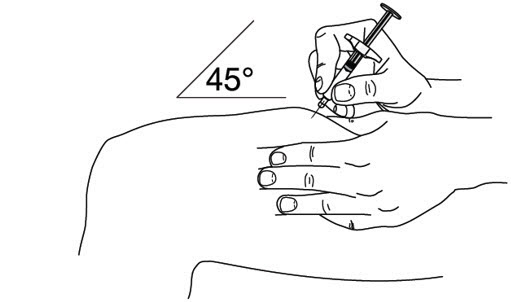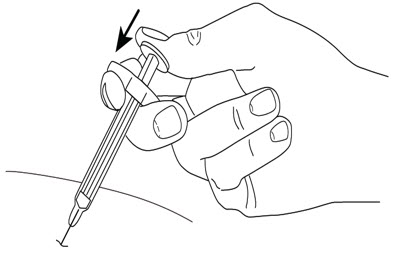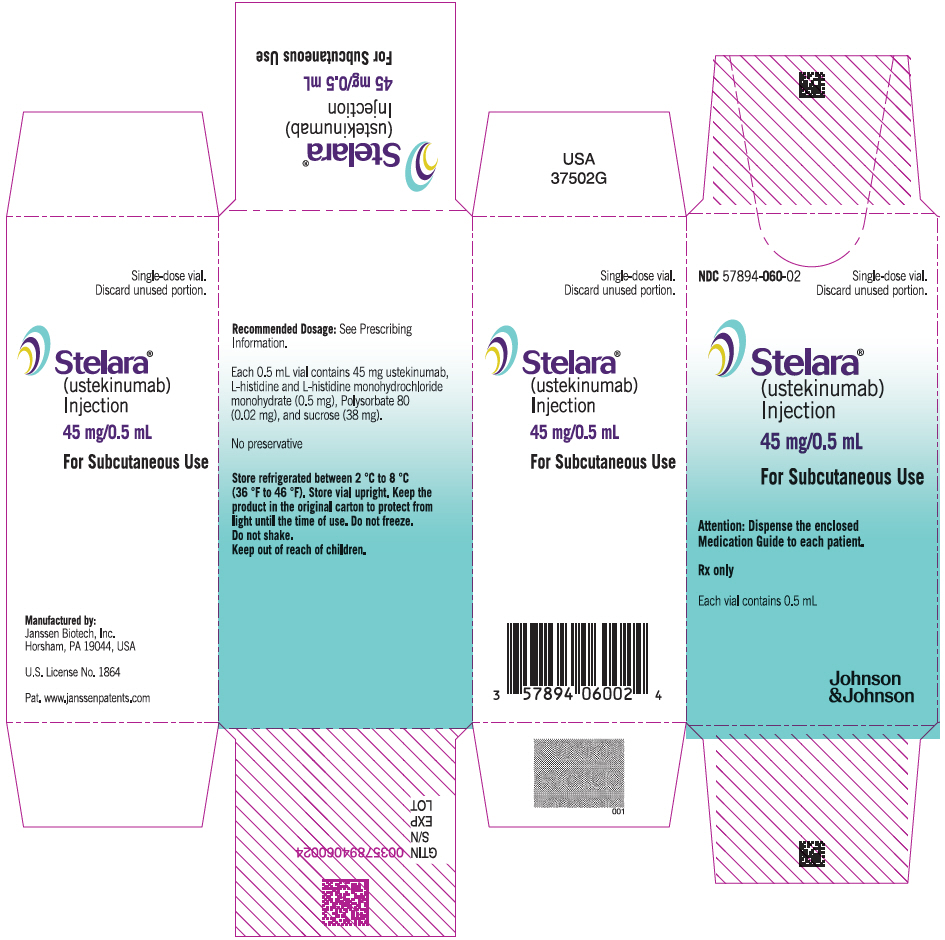 DRUG LABEL: STELARA
NDC: 57894-061 | Form: INJECTION, SOLUTION
Manufacturer: Janssen Biotech, Inc.
Category: prescription | Type: HUMAN PRESCRIPTION DRUG LABEL
Date: 20260128

ACTIVE INGREDIENTS: USTEKINUMAB 90 mg/1 mL
INACTIVE INGREDIENTS: SUCROSE 76 mg/1 mL; POLYSORBATE 80 0.04 mg/1 mL; HISTIDINE 1 mg/1 mL; HISTIDINE MONOHYDROCHLORIDE MONOHYDRATE; WATER

HIGHLIGHTS OF PRESCRIBING INFORMATION

These highlights do not include all the information needed to use STELARA safely and effectively. See full prescribing information for STELARA.
STELARA®(ustekinumab) injection, for subcutaneous or intravenous use
Initial U.S. Approval: 2009

RECENT MAJOR CHANGES

Warnings and Precautions Serious Hypersensitivity Reactions (5.5) | 11/2025

1 INDICATIONS AND USAGE

STELARA is a human interleukin-12 and -23 antagonist indicated for the treatment of:

Adult patients with:

- moderate to severe plaque psoriasis (PsO)who are candidates for phototherapy or systemic therapy. (1.1)
- active psoriatic arthritis (PsA). (1.2)
- moderately to severely active Crohn's disease (CD). (1.3)
- moderately to severely active ulcerative colitis.(1.4)

Pediatric patients 6 years and older with:

- moderate to severe plaque psoriasis (PsO), who are candidates for phototherapy or systemic therapy. (1.1)
- active psoriatic arthritis (PsA). (1.2)

2 DOSAGE AND ADMINISTRATION

Adult Patients with Plaque Psoriasis Subcutaneous Recommended Dosage (2.1) :

Weight Range (kilograms) | Dosage
less than or equal to 100 kg | 45 mg administered subcutaneously initially and 4 weeks later, followed by 45 mg administered subcutaneously every 12 weeks
greater than 100 kg | 90 mg administered subcutaneously initially and 4 weeks later, followed by 90 mg administered subcutaneously every 12 weeks

Pediatric Patients 6 Years of Age and Older with Plaque Psoriasis Subcutaneous Recommended Dosage (2.1) : Weight-based dosing is recommended at the initial dose, 4 weeks later, then every 12 weeks thereafter.

Weight Range (kilograms) | Dose
less than 60 kg | 0.75 mg/kg
60 kg to 100 kg | 45 mg
greater than 100 kg | 90 mg

Psoriatic Arthritis Adult Subcutaneous Recommended Dosage (2.2):

- The recommended dosage is 45 mg administered subcutaneously initially and 4 weeks later, followed by 45 mg administered subcutaneously every 12 weeks.
- For patients with co-existent moderate-to-severe plaque psoriasis weighing greater than 100 kg, the recommended dosage is 90 mg administered subcutaneously initially and 4 weeks later, followed by 90 mg administered subcutaneously every 12 weeks.

Psoriatic Arthritis Pediatric 6 years of Age and Older Subcutaneous Recommended Dosage (2.2): Weight-based dosing is recommended at the initial dose, 4 weeks later, then every 12 weeks thereafter.

Weight Range (kilograms) | Dose
less than 60 kg | 0.75 mg/kg
60 kg or more | 45 mg
greater than 100 kg with co-existent moderate-to-severe plaque psoriasis | 90 mg

Crohn's Disease and Ulcerative Colitis Initial Adult Intravenous Recommended Dose (2.3) :

A single intravenous infusion using weight-based dosing:

Weight Range (kilograms) | Recommended Dose
up to 55 kg | 260 mg (2 vials)
greater than 55 kg to 85 kg | 390 mg (3 vials)
greater than 85 kg | 520 mg (4 vials)

Crohn's Disease and Ulcerative Colitis Maintenance Adult Subcutaneous Recommended Dosage (2.3) :

A subcutaneous 90 mg dose 8 weeks after the initial intravenous dose, then every 8 weeks thereafter.

3 DOSAGE FORMS AND STRENGTHS

Subcutaneous Injection (3)

- Injection: 45 mg/0.5 mL or 90 mg/mL solution in a single-dose prefilled syringe
- Injection: 45 mg/0.5 mL solution in a single-dose vial

Intravenous Infusion (3)

- Injection: 130 mg/26 mL (5 mg/mL) solution in a single-dose vial (3)

4 CONTRAINDICATIONS

Clinically significant hypersensitivity to ustekinumab or to any of the excipients in STELARA. (4)

5 WARNINGS AND PRECAUTIONS

- Infections: Serious infections have occurred. Avoid starting STELARA during any clinically important active infection. If a serious infection or clinically significant infection develops, discontinue STELARA until the infection resolves. (5.1)
- Theoretical Risk for Particular Infections: Serious infections from mycobacteria, salmonella, and Bacillus Calmette-Guerin (BCG) vaccinations have been reported in patients genetically deficient in IL-12/IL-23. Consider diagnostic tests for these infections as dictated by clinical circumstances. (5.2)
- Tuberculosis (TB): Evaluate patients for TB prior to initiating treatment with STELARA. Initiate treatment of latent TB before administering STELARA. (5.3)
- Malignancies: STELARA may increase risk of malignancy. The safety of STELARA in patients with a history of or a known malignancy has not been evaluated. (5.4)
- Serious Hypersensitivity Reactions: If a severe or other clinically significant hypersensitivity reaction occurs, discontinue STELARA immediately and initiate appropriate medical treatment. (5.5)
- Posterior Reversible Encephalopathy Syndrome (PRES): If PRES is suspected, treat promptly, and discontinue STELARA. (5.6)
- Immunizations:Avoid use of live vaccines in patients during treatment with STELARA . (5.7)
- Noninfectious Pneumonia: Cases of interstitial pneumonia, eosinophilic pneumonia, and cryptogenic organizing pneumonia have been reported during post-approval use of STELARA. If diagnosis is confirmed, discontinue STELARA and institute appropriate treatment. (5.8)

6 ADVERSE REACTIONS

Most common adverse reactions are:

- Psoriasis and Psoriatic Arthritis (≥3%): nasopharyngitis, upper respiratory tract infection, headache, and fatigue. (6.1)
- Crohn's Disease, induction (≥3%): vomiting. (6.1)
- Crohn's Disease, maintenance (≥3%): nasopharyngitis, injection site erythema, vulvovaginal candidiasis/mycotic infection, bronchitis, pruritus, urinary tract infection, and sinusitis. (6.1)
- Ulcerative colitis, induction (≥3%): nasopharyngitis. (6.1)
- Ulcerative colitis, maintenance (≥3%): nasopharyngitis, headache, abdominal pain, influenza, fever, diarrhea, sinusitis, fatigue, and nausea. (6.1)

To report SUSPECTED ADVERSE REACTIONS, contact Janssen Biotech, Inc. at 1-800-526-7736 or FDA at 1-800-FDA-1088 or www.fda.gov/medwatch.

FULL PRESCRIBING INFORMATION

1 INDICATIONS AND USAGE

1.1 Plaque Psoriasis (PsO)

STELARA is indicated for the treatment of adults and pediatric patients 6 years of age and older with moderate to severe plaque psoriasis who are candidates for phototherapy or systemic therapy.

1.2 Psoriatic Arthritis (PsA)

STELARA is indicated for the treatment of adults and pediatric patients 6 years of age and older with active psoriatic arthritis.

1.3 Crohn's Disease (CD)

STELARA is indicated for the treatment of adult patients with moderately to severely active Crohn's disease.

1.4 Ulcerative Colitis

STELARA is indicated for the treatment of adult patients with moderately to severely active ulcerative colitis.

2 DOSAGE AND ADMINISTRATION

2.1 Recommended Dosage in Plaque Psoriasis

Subcutaneous Adult Dosage Regimen

- For patients weighing 100 kg or less, the recommended dosage is 45 mg initially and 4 weeks later, followed by 45 mg every 12 weeks.
- For patients weighing more than 100 kg, the recommended dosage is 90 mg initially and 4 weeks later, followed by 90 mg every 12 weeks.

In subjects weighing more than 100 kg, 45 mg was also shown to be efficacious. However, 90 mg resulted in greater efficacy in these subjects [see Clinical Studies (14)] .

Subcutaneous Pediatric Dosage Regimen

Administer STELARA subcutaneously at Weeks 0 and 4, then every 12 weeks thereafter.

The recommended dose of STELARA for pediatric patients 6 years of age and older with plaque psoriasis based on body weight is shown below (Table 1).

Table 1: Recommended Dose of STELARA for Subcutaneous Injection in Pediatric Patients 6 Years of Age and Older With Plaque Psoriasis
Body Weight of Patient at the Time of Dosing | Recommended Dose
less than 60 kg | 0.75 mg/kg
60 kg to 100 kg | 45 mg
more than 100 kg | 90 mg

For pediatric patients weighing less than 60 kg, the administration volume for the recommended dose (0.75 mg/kg) is shown in Table 2; withdraw the appropriate volume from the vial.

Table 2: Injection volumes of STELARA 45 mg/0.5 mL Vials for Pediatric Patients 6 Years of Age and Older With Plaque Psoriasis and Pediatric Patients 6 Years of Age and Older With Psoriatic Arthritis [Refer to 2.2 Psoriatic Arthritis; Subcutaneous Pediatric Dosage Regimen.] Weighing Less Than 60 kg
Body Weight (kg) at the time of dosing | Dose (mg) | Volume of injection (mL)
15 | 11.3 | 0.12
16 | 12 | 0.13
17 | 12.8 | 0.14
18 | 13.5 | 0.15
19 | 14.3 | 0.16
20 | 15 | 0.17
21 | 15.8 | 0.17
22 | 16.5 | 0.18
23 | 17.3 | 0.19
24 | 18 | 0.20
25 | 18.8 | 0.21
26 | 19.5 | 0.22
27 | 20.3 | 0.22
28 | 21 | 0.23
29 | 21.8 | 0.24
30 | 22.5 | 0.25
31 | 23.3 | 0.26
32 | 24 | 0.27
33 | 24.8 | 0.27
34 | 25.5 | 0.28
35 | 26.3 | 0.29
36 | 27 | 0.3
37 | 27.8 | 0.31
38 | 28.5 | 0.32
39 | 29.3 | 0.32
40 | 30 | 0.33
41 | 30.8 | 0.34
42 | 31.5 | 0.35
43 | 32.3 | 0.36
44 | 33 | 0.37
45 | 33.8 | 0.37
46 | 34.5 | 0.38
47 | 35.3 | 0.39
48 | 36 | 0.4
49 | 36.8 | 0.41
50 | 37.5 | 0.42
51 | 38.3 | 0.42
52 | 39 | 0.43
53 | 39.8 | 0.44
54 | 40.5 | 0.45
55 | 41.3 | 0.46
56 | 42 | 0.46
57 | 42.8 | 0.47
58 | 43.5 | 0.48
59 | 44.3 | 0.49

2.2 Recommended Dosage in Psoriatic Arthritis

Subcutaneous Adult Dosage Regimen

- The recommended dosage is 45 mg initially and 4 weeks later, followed by 45 mg every 12 weeks.
- For patients with co-existent moderate-to-severe plaque psoriasis weighing more than 100 kg, the recommended dosage is 90 mg initially and 4 weeks later, followed by 90 mg every 12 weeks.

Subcutaneous Pediatric Dosage Regimen

Administer STELARA subcutaneously at Weeks 0 and 4, then every 12 weeks thereafter.

The recommended dose of STELARA for pediatric patients 6 years of age and older with psoriatic arthritis, based on body weight, is shown below (Table 3).

Table 3: Recommended Dose of STELARA for Subcutaneous Injection in Pediatric Patients 6 Years of Age and Older With Psoriatic Arthritis
Body Weight of Patient at the Time of Dosing | Recommended Dose
less than 60 kg [For pediatric patients weighing less than 60 kg, the administration volume for the recommended dose (0.75 mg/kg) is shown in Table 2; withdraw the appropriate volume from the vial.] | 0.75 mg/kg
60 kg or more | 45 mg
greater than 100 kg with co-existent moderate-to-severe plaque psoriasis | 90 mg

2.3 Recommended Dosage in Crohn's Disease and Ulcerative Colitis

Intravenous Induction Adult Dosage Regimen

A single intravenous infusion dose of STELARA using the weight-based dosage regimen specified in Table 4 [see Instructions for dilution of STELARA 130 mg vial for intravenous infusion (2.5)] .

Table 4: Initial Intravenous Dosage of STELARA
Body Weight of Patient at the time of dosing | Dose | Number of 130 mg/26 mL (5 mg/mL) STELARA vials
55 kg or less | 260 mg | 2
more than 55 kg to 85 kg | 390 mg | 3
more than 85 kg | 520 mg | 4

Subcutaneous Maintenance Adult Dosage Regimen

The recommended maintenance dosage is a subcutaneous 90 mg dose administered 8 weeks after the initial intravenous dose, then every 8 weeks thereafter.

2.4 General Considerations for Administration

- STELARA is intended for use under the guidance and supervision of a healthcare provider . STELARA should only be administered to patients who will be closely monitored and have regular follow-up visits with a healthcare provider. The appropriate dose should be determined by a healthcare provider using the patient's current weight at the time of dosing. In pediatric patients, it is recommended that STELARA be administered by a healthcare provider. If a healthcare provider determines that it is appropriate, a patient may self-inject or a caregiver may inject STELARA after proper training in subcutaneous injection technique. Instruct patients to follow the directions provided in the Instructions for Use [see Instructions for Use].
- The needle cover on the prefilled syringe contains dry natural rubber (a derivative of latex). The needle cover should not be handled by persons sensitive to latex.
- It is recommended that each injection be administered at a different anatomic location (such as upper arms, gluteal regions, thighs, or any quadrant of abdomen) than the previous injection, and not into areas where the skin is tender, bruised, erythematous, or indurated. When using the vial, a 1 mL syringe with a 27 gauge, ½ inch needle is recommended.
- Prior to administration, visually inspect STELARA for particulate matter and discoloration. STELARA is a colorless to light yellow solution and may contain a few small translucent or white particles. Do not use STELARA if it is discolored or cloudy, or if other particulate matter is present. STELARA does not contain preservatives; therefore, discard any unused product remaining in the vial and/or syringe.

2.5 Preparation and Administration of STELARA 130 mg/26 mL (5 mg/mL) Vial for Intravenous Infusion (Crohn's Disease and Ulcerative Colitis)

STELARA solution for intravenous infusion must be diluted, prepared, and infused by a healthcare professional using aseptic technique.

1. Calculate the dose and the number of STELARA vials needed based on patient weight (Table 4). Each 26 mL vial of STELARA contains 130 mg of ustekinumab.
2. Withdraw, and then discard a volume of the 0.9% Sodium Chloride Injection, USP from the 250 mL infusion bag equal to the volume of STELARA to be added (discard 26 mL sodium chloride for each vial of STELARA needed, for 2 vials- discard 52 mL, for 3 vials- discard 78 mL, 4 vials- discard 104 mL). Alternatively, a 250 mL infusion bag containing 0.45% Sodium Chloride Injection, USP may be used.
3. Withdraw 26 mL of STELARA from each vial needed and add it to the 250 mL infusion bag. The final volume in the infusion bag should be 250 mL. Gently mix.
4. Visually inspect the diluted solution before infusion. Do not use if visibly opaque particles, discoloration or foreign particles are observed.
5. Infuse the diluted solution over a period of at least one hour. Once diluted, the infusion should be completely administered within eight hours of the dilution in the infusion bag.
6. Use only an infusion set with an in-line, sterile, non-pyrogenic, low protein-binding filter (pore size 0.2 micrometer).
7. Do not infuse STELARA concomitantly in the same intravenous line with other agents.
8. STELARA does not contain preservatives. Each vial is for a one-time use in only one patient. Discard any remaining solution. Dispose any unused medicinal product in accordance with local requirements.

Storage

If necessary, the diluted infusion solution may be kept at room temperature up to 25 °C (77 °F) for up to 7 hours. Storage time at room temperature begins once the diluted solution has been prepared. The infusion should be completed within 8 hours after the dilution in the infusion bag (cumulative time after preparation including the storage and the infusion period). Do not freeze. Discard any unused portion of the infusion solution.

3 DOSAGE FORMS AND STRENGTHS

STELARA (ustekinumab) is a colorless to light yellow solution and may contain a few small translucent or white particles.

Subcutaneous Injection

- Injection: 45 mg/0.5 mL or 90 mg/mL solution in a single-dose prefilled syringe
- Injection: 45 mg/0.5 mL solution in a single-dose vial

Intravenous Infusion

- Injection: 130 mg/26 mL (5 mg/mL) solution in a single-dose vial

4 CONTRAINDICATIONS

STELARA is contraindicated in patients with clinically significant hypersensitivity to ustekinumab or to any of the excipients in STELARA [see Warnings and Precautions (5.5)].

5 WARNINGS AND PRECAUTIONS

5.1 Infections

STELARA may increase the risk of infections and reactivation of latent infections. Serious bacterial, mycobacterial, fungal, and viral infections were observed in patients receiving STELARA [see Adverse Reactions (6.1, 6.3)] .

Serious infections requiring hospitalization, or otherwise clinically significant infections, reported in clinical trials included the following:

- Plaque Psoriasis: diverticulitis, cellulitis, pneumonia, appendicitis, cholecystitis, sepsis, osteomyelitis, viral infections, gastroenteritis, and urinary tract infections.
- Psoriatic arthritis: cholecystitis.
- Crohn's disease: anal abscess, gastroenteritis, ophthalmic herpes zoster, pneumonia, and listeria meningitis.
- Ulcerative colitis: gastroenteritis, ophthalmic herpes zoster, pneumonia, and listeriosis.

Avoid initiating treatment with STELARA in patients with any clinically important active infection until the infection resolves or is adequately treated. Consider the risks and benefits of treatment prior to initiating use of STELARA in patients with a chronic infection or a history of recurrent infection.

Instruct patients to seek medical advice if signs or symptoms suggestive of an infection occur while on treatment with STELARA and discontinue STELARA for serious or clinically significant infections until the infection resolves or is adequately treated.

5.2 Theoretical Risk for Vulnerability to Particular Infections

Individuals genetically deficient in IL-12/IL-23 are particularly vulnerable to disseminated infections from mycobacteria (including nontuberculous, environmental mycobacteria), salmonella (including nontyphi strains), and Bacillus Calmette-Guerin (BCG) vaccinations. Serious infections and fatal outcomes have been reported in such patients.

It is not known whether patients with pharmacologic blockade of IL-12/IL-23 from treatment with STELARA may be susceptible to these types of infections. Consider appropriate diagnostic testing, (e.g., tissue culture, stool culture, as dictated by clinical circumstances).

5.3 Pre-treatment Evaluation for Tuberculosis

Evaluate patients for tuberculosis infection prior to initiating treatment with STELARA.

Avoid administering STELARA to patients with active tuberculosis infection. Initiate treatment of latent tuberculosis prior to administering STELARA. Consider anti-tuberculosis therapy prior to initiation of STELARA in patients with a past history of latent or active tuberculosis in whom an adequate course of treatment cannot be confirmed. Closely monitor patients receiving STELARA for signs and symptoms of active tuberculosis during and after treatment.

5.4 Malignancies

STELARA is an immunosuppressant and may increase the risk of malignancy. Malignancies were reported among subjects who received STELARA in clinical trials [see Adverse Reactions (6.1)] . In rodent models, inhibition of IL-12/IL-23p40 increased the risk of malignancy [see Nonclinical Toxicology (13)] .

The safety of STELARA has not been evaluated in patients who have a history of malignancy or who have a known malignancy.

There have been post-marketing reports of the rapid appearance of multiple cutaneous squamous cell carcinomas in patients receiving STELARA who had pre-existing risk factors for developing non-melanoma skin cancer. Monitor all patients receiving STELARA for the appearance of non-melanoma skin cancer. Closely follow patients greater than 60 years of age, those with a medical history of prolonged immunosuppressant therapy and those with a history of PUVA treatment [see Adverse Reactions (6.1)] .

5.5 Serious Hypersensitivity Reactions

Serious hypersensitivity reactions, including anaphylaxis and angioedema, have been reported with STELARA in clinical trials and postmarketing. Some serious hypersensitivity reactions have occurred during the first intravenous dose of STELARA [see Adverse Reactions (6.1, 6.3)].

If a severe or clinically significant hypersensitivity reaction occurs, discontinue STELARA immediately and initiate appropriate medical treatment [see Contraindications (4)].

5.6 Posterior Reversible Encephalopathy Syndrome (PRES)

Two cases of posterior reversible encephalopathy syndrome (PRES), also known as Reversible Posterior Leukoencephalopathy Syndrome (RPLS), were reported in clinical trials. Cases have also been reported in postmarketing experience in patients with psoriasis, psoriatic arthritis, and Crohn's disease. Clinical presentation included headaches, seizures, confusion, visual disturbances, and imaging changes consistent with PRES a few days to several months after ustekinumab initiation. A few cases reported latency of a year or longer. Patients recovered with supportive care following withdrawal of ustekinumab.

Monitor all patients treated with STELARA for signs and symptoms of PRES. If PRES is suspected, promptly administer appropriate treatment and discontinue STELARA.

5.7 Immunizations

Prior to initiating therapy with STELARA, patients should receive all age-appropriate immunizations as recommended by current immunization guidelines. Patients being treated with STELARA should avoid receiving live vaccines. Avoid administering BCG vaccines during treatment with STELARA or for one year prior to initiating treatment or one year following discontinuation of treatment. Caution is advised when administering live vaccines to household contacts of patients receiving STELARA because of the potential risk for shedding from the household contact and transmission to patient.

Non-live vaccinations received during a course of STELARA may not elicit an immune response sufficient to prevent disease.

5.8 Noninfectious Pneumonia

Cases of interstitial pneumonia, eosinophilic pneumonia, and cryptogenic organizing pneumonia have been reported during post-approval use of STELARA. Clinical presentations included cough, dyspnea, and interstitial infiltrates following one to three doses. Serious outcomes have included respiratory failure and prolonged hospitalization. Patients improved with discontinuation of therapy and in certain cases administration of corticosteroids. If diagnosis is confirmed, discontinue STELARA and institute appropriate treatment [see Postmarketing Experience (6.3)] .

6 ADVERSE REACTIONS

The following serious adverse reactions are discussed elsewhere in the label:

- Infections [see Warnings and Precautions (5.1)]
- Malignancies [see Warnings and Precautions (5.4)]
- Serious Hypersensitivity Reactions [see Warnings and Precautions (5.5)]
- Posterior Reversible Encephalopathy Syndrome (PRES) [see Warnings and Precautions (5.6)]
- Noninfectious Pneumonia [see Warnings and Precautions (5.8)]

6.1 Clinical Trials Experience

Because clinical trials are conducted under widely varying conditions, adverse reaction rates observed in the clinical trials of a drug cannot be directly compared to rates in the clinical trials of another drug and may not reflect the rates observed in practice.

Adult Subjects with Plaque Psoriasis

The safety data reflect exposure to STELARA in 3117 adult subjects with plaque psoriasis, including 2414 exposed for at least 6 months, 1855 exposed for at least one year, 1653 exposed for at least two years, 1569 exposed for at least three years, 1482 exposed for at least four years and 838 exposed for at least five years.

Table 5 summarizes the adverse reactions that occurred at a rate of at least 1% with higher rates in the STELARA groups during the placebo-controlled period of Ps STUDY 1 and Ps STUDY 2 [see Clinical Studies (14)] .

Table 5: Adverse Reactions, Reported by ≥1% of Subjects with Plaque Psoriasis and at Higher Rates in the STELARA groups through Week 12 in Ps STUDY 1 and Ps STUDY 2
 |  | STELARA
 | Placebo | 45 mg | 90 mg
Subjects treated | 665 | 664 | 666
Nasopharyngitis | 51 (8%) | 56 (8%) | 49 (7%)
Upper respiratory tract infection | 30 (5%) | 36 (5%) | 28 (4%)
Headache | 23 (3%) | 33 (5%) | 32 (5%)
Fatigue | 14 (2%) | 18 (3%) | 17 (3%)
Back pain | 8 (1%) | 9 (1%) | 14 (2%)
Dizziness | 8 (1%) | 8 (1%) | 14 (2%)
Pharyngolaryngeal pain | 7 (1%) | 9 (1%) | 12 (2%)
Pruritus | 9 (1%) | 10 (2%) | 9 (1%)
Injection site erythema | 3 (<1%) | 6 (1%) | 13 (2%)
Myalgia | 4 (1%) | 7 (1%) | 8 (1%)
Depression | 3 (<1%) | 8 (1%) | 4 (1%)

Adverse reactions that occurred at rates less than 1% in the controlled period of Ps STUDIES 1 and 2 through week 12 included: cellulitis, herpes zoster, diverticulitis, and certain injection site reactions (pain, swelling, pruritus, induration, hemorrhage, bruising, and irritation).

One case of PRES occurred during clinical trials in adult subjects with plaque psoriasis [see Warnings and Precautions (5.6)] .

Infections

In the placebo-controlled period of clinical trials of subjects with plaque psoriasis (average follow-up of 12.6 weeks for subjects receiving placebo and 13.4 weeks for STELARA-treated subjects), 27% of STELARA-treated subjects reported infections (1.39 per patient-years of follow-up) compared with 24% of subjects receiving placebo (1.21 per patient-years of follow-up). Serious infections occurred in 0.3% of STELARA-treated subjects (0.01 per patient-years of follow-up) and in 0.4% of subjects receiving placebo (0.02 per patient-year of follow-up) [see Warnings and Precautions (5.1)] .

In the controlled and non-controlled portions of clinical trials in subjects with plaque psoriasis (median follow-up of 3.2 years), representing 8998 patient-years of exposure, 72.3% of STELARA-treated subjects reported infections (0.87 per patient-years of follow-up). Serious infections were reported in 2.8% of subjects (0.01 per patient-years of follow-up).

Malignancies

In the controlled and non-controlled portions of clinical trials in subjects with plaque psoriasis (median follow-up of 3.2 years, representing 8998 patient-years of exposure), 1.7% of STELARA-treated subjects reported malignancies excluding non-melanoma skin cancers (0.60 per hundred patient-years of follow-up). Non-melanoma skin cancer was reported in 1.5% of STELARA-treated subjects (0.52 per hundred patient-years of follow-up) [see Warnings and Precautions (5.4)] . The most frequently observed malignancies other than non-melanoma skin cancer during the clinical trials were: prostate, melanoma, colorectal and breast. Malignancies other than non-melanoma skin cancer in STELARA-treated subjects during the controlled and uncontrolled portions of trials were similar in type and number to what would be expected in the general U.S. population according to the SEER database (adjusted for age, gender and race).^1

Pediatric Subjects with Plaque Psoriasis

The safety of STELARA was assessed in two trials of pediatric subjects with moderate to severe plaque psoriasis. Ps STUDY 3 evaluated safety for up to 60 weeks in 110 pediatric subjects 12 to 17 years old. Ps STUDY 4 evaluated safety for up to 56 weeks in 44 pediatric subjects 6 to 11 years old. The safety profile in pediatric subjects was similar to the safety profile from trials in adults with plaque psoriasis.

Psoriatic Arthritis

The safety of STELARA was assessed in 927 subjects in two randomized, double-blind, placebo-controlled trials in adults with active psoriatic arthritis (PsA). The overall safety profile of STELARA in subjects with PsA was consistent with the safety profile seen in clinical trials in adult subjects with plaque psoriasis. A higher incidence of arthralgia, nausea, and dental infections was observed in STELARA-treated subjects when compared with placebo-treated subjects (3% vs. 1% for arthralgia and 3% vs. 1% for nausea; 1% vs. 0.6% for dental infections) in the placebo-controlled portions of the PsA clinical trials.

Crohn's Disease

The safety of STELARA was assessed in 1407 subjects with moderately to severely active Crohn's disease (Crohn's Disease Activity Index [CDAI] greater than or equal to 220 and less than or equal to 450) in three randomized, double-blind, placebo-controlled, parallel-group, multicenter trials. These 1407 subjects included 40 subjects who received a prior investigational intravenous ustekinumab formulation but were not included in the efficacy analyses. In trials CD-1 and CD-2 there were 470 subjects who received STELARA 6 mg/kg as a weight-based single intravenous induction dose and 466 who received placebo [see Dosage and Administration (2.3)] . Subjects who were responders in either trial CD-1 or CD-2 were randomized to receive a subcutaneous maintenance regimen of either 90 mg STELARA every 8 weeks, or placebo for 44 weeks in trial CD-3. Subjects in these 3 trials may have received other concomitant therapies including aminosalicylates, immunomodulatory agents [azathioprine (AZA), 6-mercaptopurine (6-MP), methotrexate (MTX)], oral corticosteroids (prednisone or budesonide), and/or antibiotics for their Crohn's disease [see Clinical Studies (14.4)] .

The overall safety profile of STELARA was consistent with the safety profile seen in the clinical trials in adult subjects with plaque psoriasis and psoriatic arthritis. Common adverse reactions in trials CD-1 and CD-2 and in trial CD-3 are listed in Tables 6 and 7, respectively.

Table 6: Common Adverse Reactions Through Week 8 in Trials CD-1 and CD-2 occurring in ≥3% of STELARA-Treated Subjects and Higher Than Subjects Receiving Placebo
 | Placebo | STELARA 6 mg/kg single intravenous induction dose
 | N=466 | N=470
Vomiting | 3% | 4%

Other less common adverse reactions reported in subjects in trials CD-1 and CD-2 included asthenia (1% vs 0.4%), acne (1% vs 0.4%), and pruritus (2% vs 0.4%).

Table 7: Common Adverse Reactions Through Week 44 in Trial CD-3 occurring in ≥3% of STELARA-Treated Subjects and Higher Than Subjects Receiving Placebo
 | Placebo | STELARA 90 mg subcutaneous maintenance dose every 8 weeks
 | N=133 | N=131
Nasopharyngitis | 8% | 11%
Injection site erythema | 0 | 5%
Vulvovaginal candidiasis/mycotic infection | 1% | 5%
Bronchitis | 3% | 5%
Pruritus | 2% | 4%
Urinary tract infection | 2% | 4%
Sinusitis | 2% | 3%

Infections

In subjects with Crohn's disease, serious or other clinically significant infections included anal abscess, gastroenteritis, and pneumonia. In addition, listeria meningitis and ophthalmic herpes zoster were reported in one subject each [see Warnings and Precautions (5.1)] .

Malignancies

With up to one year of treatment in the Crohn's disease clinical trials, 0.2% of STELARA-treated subjects (0.36 events per hundred patient-years) and 0.2% of placebo-treated subjects (0.58 events per hundred patient-years) developed non-melanoma skin cancer. Malignancies other than non-melanoma skin cancers occurred in 0.2% of STELARA-treated subjects (0.27 events per hundred patient-years) and in none of the placebo-treated subjects.

Hypersensitivity Reactions Including Anaphylaxis

In CD trials, two subjects reported hypersensitivity reactions following STELARA administration. One subject experienced signs and symptoms consistent with anaphylaxis (tightness of the throat, shortness of breath, and flushing) after a single subcutaneous administration (0.1% of subjects receiving subcutaneous STELARA). In addition, one subject experienced signs and symptoms consistent with or related to a hypersensitivity reaction (chest discomfort, flushing, urticaria, and increased body temperature) after the initial intravenous STELARA dose (0.08% of subjects receiving intravenous STELARA). These subjects were treated with oral antihistamines or corticosteroids and in both cases symptoms resolved within an hour [see Warnings and Precautions (5.5)].

Ulcerative Colitis

The safety of STELARA was evaluated in two randomized, double-blind, placebo-controlled clinical trials (UC-1 [IV induction] and UC-2 [SC maintenance]) in 960 adult subjects with moderately to severely active ulcerative colitis [see Clinical Studies (14.5)] . The overall safety profile of STELARA in subjects with ulcerative colitis was consistent with the safety profile seen across all approved indications. Adverse reactions reported in at least 3% of STELARA-treated subjects and at a higher rate than placebo were:

- Induction (UC-1): nasopharyngitis (7% vs 4%).
- Maintenance (UC-2): nasopharyngitis (24% vs 20%), headache (10% vs 4%), abdominal pain (7% vs 3%), influenza (6% vs 5%), fever (5% vs. 4%), diarrhea (4% vs 1%), sinusitis (4% vs 1%), fatigue (4% vs 2%), and nausea (3% vs 2%).

Infections

In subjects with ulcerative colitis, serious or other clinically significant infections included gastroenteritis and pneumonia. In addition, listeriosis and ophthalmic herpes zoster were reported in one subject each [see Warnings and Precautions (5.1)] .

Malignancies

With up to one year of treatment in the ulcerative colitis clinical trials, 0.4% of STELARA-treated subjects (0.48 events per hundred patient-years) and 0.0% of subjects receiving placebo (0.00 events per hundred patient-years) developed non-melanoma skin cancer. Malignancies other than non-melanoma skin cancers occurred in 0.5% of STELARA-treated subjects (0.64 events per hundred patient-years) and 0.2% of subjects receiving placebo (0.40 events per hundred patient-years).

6.2 Immunogenicity

The observed incidence of anti-drug antibodies is highly dependent on the sensitivity and specificity of the assay. Differences in assay methods preclude meaningful comparisons of the incidence of anti-drug antibodies in the studies described below with the incidence of anti-drug antibodies in studies of other ustekinumab products.

Approximately 6 to 12.4% of subjects treated with STELARA in clinical trials in subjects with plaque psoriasis and psoriatic arthritis developed antibodies to ustekinumab, which were generally low-titer. In clinical trials in subjects with plaque psoriasis, antibodies to ustekinumab were associated with reduced or undetectable serum ustekinumab concentrations and reduced efficacy. In trials in subjects with plaque psoriasis, the majority of subjects who were positive for antibodies to ustekinumab had neutralizing antibodies.

In clinical trials in subjects with Crohn’s disease and ulcerative colitis, 2.9% and 4.6% of subjects, respectively, developed antibodies to ustekinumab when treated with STELARA for approximately one year. No apparent association between the development of antibodies to ustekinumab and the development of injection site reactions was seen.

6.3 Postmarketing Experience

The following adverse reactions have been reported during post-approval use of STELARA. Because these reactions are reported voluntarily from a population of uncertain size, it is not always possible to reliably estimate their frequency or establish a causal relationship to STELARA exposure.

Immune system disorders: Hypersensitivity reactions (e.g., anaphylaxis, angioedema, dyspnea, rash, urticaria), including a fatal case that presented with chest tightness and dyspnea during infusion of the first dose.

Infections and infestations:Lower respiratory tract infection (including opportunistic fungal infections and tuberculosis).

Neurological disorders:Posterior Reversible Encephalopathy Syndrome (PRES) .

Respiratory, thoracic, and mediastinal disorders:Interstitial pneumonia, eosinophilic pneumonia, and cryptogenic organizing pneumonia.

Skin reactions: Pustular psoriasis, erythrodermic psoriasis, hypersensitivity vasculitis.

7 DRUG INTERACTIONS

7.1 Concomitant Therapies

In trials in subjects with plaque psoriasis the safety of STELARA in combination with immunosuppressive agents or phototherapy has not been evaluated . In trials in subjects with psoriatic arthritis, concomitant MTX use did not appear to influence the safety or efficacy of STELARA. In trials in subjects with Crohn's disease (CD-1 and CD-2) and ulcerative colitis (UC-1), immunomodulators (6-MP, AZA, MTX) were used concomitantly in approximately 30% of subjects and corticosteroids were used concomitantly in approximately 40% and 50% of Crohn's disease and ulcerative colitis subjects, respectively. Use of these concomitant therapies did not appear to influence the overall safety or efficacy of STELARA.

7.2 CYP450 Substrates

The formation of CYP450 enzymes can be suppressed by increased levels of certain cytokines (e.g., IL-1, IL-6, TNFα, IFN) during chronic inflammation. Thus, use of STELARA, an antagonist of IL-12 and IL-23, could normalize the formation of CYP450 enzymes. Upon initiation or discontinuation of STELARA in patients who are receiving concomitant CYP450 substrates, particularly those with a narrow therapeutic index, consider monitoring for therapeutic effect or drug concentration and adjust the individual dosage of the CYP substrate as needed. See the prescribing information of specific CYP substrates.

A CYP-mediated drug interaction effect was not observed in subjects with Crohn’s disease [see Clinical Pharmacology (12.3)] .

7.3 Allergen Immunotherapy

STELARA has not been evaluated in patients who have undergone allergy immunotherapy. STELARA may decrease the protective effect of allergen immunotherapy (decrease tolerance) which may increase the risk of an allergic reaction to a dose of allergen immunotherapy. Therefore, caution should be exercised in patients receiving or who have received allergen immunotherapy, particularly for anaphylaxis.

8 USE IN SPECIFIC POPULATIONS

8.1 Pregnancy

Risk Summary

Available data from the Organization of Teratology Information Specialists (OTIS)/MotherToBaby STELARA Pregnancy Registry, published literature and pharmacovigilance in pregnant women have not identified a STELARA-associated risk of major birth defects, miscarriage or other adverse maternal or fetal outcomes (see Data). There are risks to the mother and the fetus associated with inflammatory bowel disease (IBD) in pregnancy. In animal reproductive and developmental toxicity studies, no adverse developmental effects were observed in offspring after administration of ustekinumab to pregnant monkeys at exposures greater than 100 times the maximum recommended human dose (MRHD).

All pregnancies have a background risk of birth defect, loss, or other adverse outcomes. In the U.S. general population, the estimated background risk of major birth defects and miscarriage of clinically recognized pregnancies is 2% to 4% and 15% to 20%, respectively.

Clinical Considerations

Disease-associated Maternal and Embryo/Fetal Risk

Published data suggest that the risk of adverse pregnancy outcomes in women with IBD is associated with increased disease activity. Adverse pregnancy outcomes include preterm delivery (before 37 weeks of gestation), low birth weight (less than 2500 g) infants, and small for gestational age at birth.

Fetal/Neonatal Adverse Reactions

Transport of endogenous IgG antibodies across the placenta increases as pregnancy progresses, and peaks during the third trimester. Therefore, STELARA may be present in infants exposed in utero. The potential clinical impact of ustekinumab exposure in infants exposed in uteroshould be considered.

Data

Human Data

An observational pregnancy registry conducted by (OTIS)/MotherToBaby in the U.S. and Canada (enrollment between 2013 and 2019) assessed the risk of major birth defects, pattern of major and minor anomalies in live-born infants, miscarriage, and adverse infant outcomes in women with STELARA exposure. In the registry study, there were 101 participants and 107 pregnancies with exposure to STELARA (88 prospective; 19 retrospective). Most participants had a primary indication of CD (65.4%) or psoriasis (30.8%). The pregnancy registry did not identify a STELARA -associated risk of major birth defects, pattern of major or minor anomalies, increased risk of miscarriage or adverse infant outcomes. Methodological limitations of the registry include small sample size, lack of an internal comparison group, a mix of prospective and retrospective reports, and unmeasured confounders. The conclusions from the pregnancy registry were consistent with the published literature and pharmacovigilance.

Animal Data

Ustekinumab was tested in two embryo-fetal development toxicity studies in cynomolgus monkeys. No teratogenic or other adverse developmental effects were observed in fetuses from pregnant monkeys that were administered ustekinumab subcutaneously twice weekly or intravenously weekly during the period of organogenesis. Serum concentrations of ustekinumab in pregnant monkeys were greater than 100 times the serum concentration in patients treated subcutaneously with 90 mg of ustekinumab weekly for 4 weeks.

In a combined embryo-fetal development and pre- and post-natal development toxicity study, pregnant cynomolgus monkeys were administered subcutaneous doses of ustekinumab twice weekly at exposures greater than 100 times the MRHD from the beginning of organogenesis to Day 33 after delivery. Neonatal deaths occurred in the offspring of one monkey administered ustekinumab at 22.5 mg/kg and one monkey dosed at 45 mg/kg. No ustekinumab-related-effects on functional, morphological, or immunological development were observed in the neonates from birth through six months of age.

8.2 Lactation

Risk Summary

Limited data from published literature suggests that ustekinumab is present in human breast milk. There are no available data on the effects of ustekinumab on milk production. The effects of local gastrointestinal exposure and limited systemic exposure in the breastfed infant to ustekinumab are unknown. No adverse effects on the breastfed infant causally related to ustekinumab have been identified in the published literature or postmarketing experience.

The developmental and health benefits of breastfeeding should be considered along with the mother's clinical need for STELARA and any potential adverse effects on the breastfed child from STELARA or from the underlying maternal condition.

8.4 Pediatric Use

Plaque Psoriasis

The safety and effectiveness of STELARA have been established for the treatment of moderate to severe plaque psoriasis in pediatric patients 6 years of age and older who are candidates for phototherapy or systemic therapy.

Use of STELARA in pediatric patients 12 to less than 17 years of age is supported by evidence from a multicenter, randomized, 60 week trial (Ps STUDY 3) that included a 12 week, double-blind, placebo-controlled, parallel group portion, in 110 pediatric subjects 12 years of age and older [see Adverse Reactions (6.1), Clinical Studies (14.2)] .

Use of STELARA in pediatric patients 6 to 11 years of age is supported by evidence from an open-label, single-arm, efficacy, safety, and pharmacokinetics trial (Ps STUDY 4) in 44 subjects [see Adverse Reactions (6.1), Pharmacokinetics (12.3)] .

The safety and effectiveness of STELARA have not been established in pediatric patients less than 6 years of age with plaque psoriasis.

Psoriatic Arthritis

The safety and effectiveness of STELARA have been established for treatment of psoriatic arthritis in pediatric patients 6 years of age and older.

Use of STELARA in these age groups is supported by evidence from adequate and well controlled trials of STELARA in adult subjects with psoriasis and PsA, pharmacokinetic data from adult subjects with psoriasis, adult subjects with PsA and pediatric subjects with psoriasis, and safety data from two clinical trials in 44 pediatric subjects 6 to 11 years old with psoriasis and 110 pediatric subjects 12 years of age and older with psoriasis. The observed pre-dose (trough) concentrations are generally comparable between adult subjects with psoriasis, adult subjects with PsA and pediatric subjects with psoriasis, and the PK exposure is expected to be comparable between adult and pediatric subjects with PsA [see Adverse Reactions (6.1), Clinical Pharmacology (12.3), and Clinical Studies (14.1, 14.2, 14.3)].

The safety and effectiveness of STELARA have not been established in pediatric patients less than 6 years old with psoriatic arthritis.

Crohn's Disease and Ulcerative Colitis

The safety and effectiveness of STELARA have not been established in pediatric patients with Crohn's disease or ulcerative colitis.

8.5 Geriatric Use

Of the 6709 subjects exposed to STELARA, a total of 340 were 65 years of age or older (183 subjects with plaque psoriasis, 65 subjects with psoriatic arthritis, 58 subjects with Crohn's disease, and 34 subjects with ulcerative colitis), and 40 subjects were 75 years of age or older. Clinical trials of STELARA did not include sufficient numbers of subjects 65 years of age and older to determine whether they respond differently from younger adult subjects.

10 OVERDOSAGE

Single doses up to 6 mg/kg intravenously have been administered in clinical trials without dose-limiting toxicity. In case of overdosage, monitor the patient for any signs or symptoms of adverse reactions or effects and institute appropriate symptomatic treatment immediately. Consider contacting the Poison Help line 1-800-222-1222 or a medical toxicologist for additional overdose management recommendations.

11 DESCRIPTION

Ustekinumab, a human IgG1κ monoclonal antibody, is a human interleukin-12 and -23 antagonist. Using DNA recombinant technology, ustekinumab is produced in a murine cell line (Sp2/0). The manufacturing process contains steps for the clearance of viruses. Ustekinumab is comprised of 1326 amino acids and has an estimated molecular mass that ranges from 148,079 to 149,690 Daltons.

STELARA®(ustekinumab) injection is a sterile, preservative-free, colorless to light yellow solution and may contain a few small translucent or white particles with pH of 5.7– 6.3.

STELARA for Subcutaneous Use

Available as 45 mg of ustekinumab in 0.5 mL and 90 mg of ustekinumab in 1 mL, supplied as a sterile solution in a single-dose prefilled syringe with a 27 gauge fixed ½ inch needle and as 45 mg of ustekinumab in 0.5 mL in a single-dose Type I glass vial with a coated stopper. The syringe is fitted with a passive needle guard and a needle cover that contains dry natural rubber (a derivative of latex).

Each 0.5 mL prefilled syringe or vial delivers 45 mg ustekinumab, L-histidine and L-histidine monohydrochloride monohydrate (0.5 mg), Polysorbate 80 (0.02 mg), and sucrose (38 mg).

Each 1 mL prefilled syringe delivers 90 mg ustekinumab, L-histidine and L-histidine monohydrochloride monohydrate (1 mg), Polysorbate 80 (0.04 mg), and sucrose (76 mg).

STELARA for Intravenous Infusion

Available as 130 mg of ustekinumab in 26 mL, supplied as a single-dose Type I glass vial with a coated stopper.

Each 26 mL vial delivers 130 mg ustekinumab, EDTA disodium salt dihydrate (0.52 mg), L-histidine (20 mg), L-histidine hydrochloride monohydrate (27 mg), L-methionine (10.4 mg), Polysorbate 80 (10.4 mg), and sucrose (2210 mg).

12 CLINICAL PHARMACOLOGY

12.1 Mechanism of Action

Ustekinumab is a human IgG1қ monoclonal antibody that binds with specificity to the p40 protein subunit used by both the IL-12 and IL-23 cytokines. IL-12 and IL-23 are naturally occurring cytokines that are involved in inflammatory and immune responses, such as natural killer cell activation and CD4+ T-cell differentiation and activation. In in vitromodels, ustekinumab was shown to disrupt IL-12 and IL-23 mediated signaling and cytokine cascades by disrupting the interaction of these cytokines with a shared cell-surface receptor chain, IL-12Rβ1. The cytokines IL-12 and IL-23 have been implicated as important contributors to the chronic inflammation that is a hallmark of Crohn's disease and ulcerative colitis. In animal models of colitis, genetic absence or antibody blockade of the p40 subunit of IL-12 and IL-23, the target of ustekinumab, was shown to be protective.

12.2 Pharmacodynamics

Plaque Psoriasis

In a small exploratory trial, a decrease was observed in the expression of mRNA of its molecular targets IL-12 and IL-23 in lesional skin biopsies measured at baseline and up to two weeks post-treatment in subjects with plaque psoriasis.

Ulcerative Colitis

In both trial UC-1 (induction) and trial UC-2 (maintenance), a positive relationship was observed between exposure and rates of clinical remission, clinical response, and endoscopic improvement. The response rate approached a plateau at the ustekinumab exposures associated with the recommended dosing regimen for maintenance treatment [see Clinical Studies (14.5)] .

12.3 Pharmacokinetics

Absorption

In adult subjects with plaque psoriasis, the median time to reach the maximum serum concentration (Tmax) was 13.5 days and 7 days, respectively, after a single subcutaneous administration of 45 mg (N=22) and 90 mg (N=24) of ustekinumab. In healthy subjects (N=30), the median Tmaxvalue (8.5 days) following a single subcutaneous administration of 90 mg of ustekinumab was comparable to that observed in subjects with plaque psoriasis.

Following multiple subcutaneous doses of STELARA in adult subjects with plaque psoriasis, steady-state serum concentrations of ustekinumab were achieved by Week 28. The mean (±SD) steady-state trough serum ustekinumab concentrations were 0.69 ± 0.69 mcg/mL for subjects less than or equal to 100 kg receiving a 45 mg dose and 0.74 ± 0.78 mcg/mL for subjects greater than 100 kg receiving a 90 mg dose. There was no apparent accumulation in serum ustekinumab concentration over time when given subcutaneously every 12 weeks.

Following the recommended intravenous induction dose, mean ±SD peak serum ustekinumab concentration was 125.2 ± 33.6 mcg/mL in subjects with Crohn's disease, and 129.1 ± 27.6 mcg/mL in subjects with ulcerative colitis. Starting at Week 8, the recommended subcutaneous maintenance dosing of 90 mg ustekinumab was administered every 8 weeks. Steady state ustekinumab concentration was achieved by the start of the second maintenance dose. There was no apparent accumulation in ustekinumab concentration over time when given subcutaneously every 8 weeks. Mean ±SD steady-state trough concentration was 2.5 ± 2.1 mcg/mL in subjects with Crohn's disease, and 3.3 ± 2.3 mcg/mL in subjects with ulcerative colitis for 90 mg ustekinumab administered every 8 weeks.

Distribution

Population pharmacokinetic analyses showed that the volume of distribution of ustekinumab in the central compartment was 2.7 L (95% CI: 2.69, 2.78) in subjects with Crohn's disease and 3.0 L (95% CI: 2.96, 3.07) in subjects with ulcerative colitis. The total volume of distribution at steady-state was 4.6 L in subjects with Crohn's disease and 4.4 L in subjects with ulcerative colitis.

Elimination

The mean (±SD) half-life ranged from 14.9 ± 4.6 to 45.6 ± 80.2 days across all trials in subjects with plaque psoriasis following subcutaneous administration. Population pharmacokinetic analyses showed that the clearance of ustekinumab was 0.19 L/day (95% CI: 0.185, 0.197) in subjects with Crohn's disease and 0.19 L/day (95% CI: 0.179, 0.192) in subjects with ulcerative colitis with an estimated median terminal half-life of approximately 19 days for both IBD (Crohn's disease and ulcerative colitis) populations.

These results indicate the pharmacokinetics of ustekinumab were similar between subjects with Crohn's disease and ulcerative colitis.

Metabolism

The metabolic pathway of ustekinumab has not been characterized. As a human IgG1κ monoclonal antibody, ustekinumab is expected to be degraded into small peptides and amino acids via catabolic pathways in the same manner as endogenous IgG.

Specific Populations

Weight

When given the same dose, subjects with plaque psoriasis or psoriatic arthritis weighing more than 100 kg had lower median serum ustekinumab concentrations compared with those subjects weighing 100 kg or less. The median trough serum concentrations of ustekinumab in subjects of higher weight (greater than 100 kg) in the 90 mg group were comparable to those in subjects of lower weight (100 kg or less) in the 45 mg group.

Age: Geriatric Population

A population pharmacokinetic analysis (N=106/1937 subjects with plaque psoriasis greater than or equal to 65 years old) was performed to evaluate the effect of age on the pharmacokinetics of ustekinumab. There were no apparent changes in pharmacokinetic parameters (clearance and volume of distribution) in subjects older than 65 years old.

Age: Pediatric Population

Following multiple recommended doses of STELARA in pediatric subjects 6 years of age and older with plaque psoriasis, steady-state serum concentrations of ustekinumab were achieved by Week 28. At Week 28, the mean ±SD steady-state trough serum ustekinumab concentrations were 0.36 ± 0.26 mcg/mL and 0.54 ± 0.43 mcg/mL, respectively, in pediatric subjects 6 to 11 years of age and pediatric subjects 12 years of age and older.

Overall, the observed steady-state ustekinumab trough concentrations in pediatric subjects with plaque psoriasis were within the range of those observed for adult subjects with plaque psoriasis and adult subjects with PsA after administration of STELARA.

Drug Interaction Studies

The effects of IL-12 or IL-23 on the regulation of CYP450 enzymes were evaluated in an in vitrostudy using human hepatocytes, which showed that IL-12 and/or IL-23 at levels of 10 ng/mL did not alter human CYP450 enzyme activities (CYP1A2, 2B6, 2C9, 2C19, 2D6, or 3A4).

No clinically significant changes in exposure of caffeine (CYP1A2 substrate), warfarin (CYP2C9 substrate), omeprazole (CYP2C19 substrate), dextromethorphan (CYP2D6 substrate), or midazolam (CYP3A substrate) were observed when used concomitantly with ustekinumab at the approved recommended dosage in subjects with Crohn’s disease [see Drug Interactions (7.2)] .

Population pharmacokinetic analyses indicated that the clearance of ustekinumab was not impacted by concomitant MTX, NSAIDs, and oral corticosteroids, or prior exposure to a TNF blocker in subjects with psoriatic arthritis.

In subjects with Crohn's disease and ulcerative colitis, population pharmacokinetic analyses did not indicate changes in ustekinumab clearance with concomitant use of corticosteroids or immunomodulators (AZA, 6-MP, or MTX); and serum ustekinumab concentrations were not impacted by concomitant use of these medications.

13 NONCLINICAL TOXICOLOGY

13.1 Carcinogenesis, Mutagenesis, Impairment of Fertility

Animal studies have not been conducted to evaluate the carcinogenic or mutagenic potential of STELARA. Published literature showed that administration of murine IL-12 caused an anti-tumor effect in mice that contained transplanted tumors and IL-12/IL-23p40 knockout mice or mice treated with anti-IL-12/IL-23p40 antibody had decreased host defense to tumors. Mice genetically manipulated to be deficient in both IL-12 and IL-23 or IL-12 alone developed UV-induced skin cancers earlier and more frequently compared to wild-type mice. The relevance of these experimental findings in mouse models for malignancy risk in humans is unknown.

No effects on fertility were observed in male cynomolgus monkeys that were administered ustekinumab at subcutaneous doses up to 45 mg/kg twice weekly (45 times the MRHD on a mg/kg basis) prior to and during the mating period. However, fertility and pregnancy outcomes were not evaluated in mated females.

No effects on fertility were observed in female mice that were administered an analogous IL-12/IL-23p40 antibody by subcutaneous administration at doses up to 50 mg/kg, twice weekly, prior to and during early pregnancy.

13.2 Animal Toxicology and/or Pharmacology

In a 26-week toxicology study, one out of 10 monkeys subcutaneously administered 45 mg/kg ustekinumab twice weekly for 26 weeks had a bacterial infection.

14 CLINICAL STUDIES

14.1 Adult Subjects with Plaque Psoriasis

Two multicenter, randomized, double-blind, placebo-controlled trials (Ps STUDY 1 and Ps STUDY 2) enrolled a total of 1996 subjects 18 years of age and older with plaque psoriasis who had a minimum body surface area involvement of 10%, and Psoriasis Area and Severity Index (PASI) score ≥12, and who were candidates for phototherapy or systemic therapy. Subjects with guttate, erythrodermic, or pustular psoriasis were excluded from the trials.

Ps STUDY 1 enrolled 766 subjects and Ps STUDY 2 enrolled 1230 subjects. The trials had the same design through Week 28. In both trials, subjects were randomized in equal proportion to placebo, 45 mg or 90 mg of STELARA. Subjects randomized to STELARA received 45 mg or 90 mg doses, regardless of weight, at Weeks 0, 4, and 16. Subjects randomized to receive placebo at Weeks 0 and 4 crossed over to receive STELARA (either 45 mg or 90 mg) at Weeks 12 and 16.

In both trials, subjects in all treatment groups had a median baseline PASI score ranging from approximately 17 to 18. Baseline PGA score was marked or severe in 44% of subjects in Ps STUDY 1 and 40% of subjects in Ps STUDY 2. Approximately two-thirds of all subjects had received prior phototherapy, 69% had received either prior conventional systemic or biologic therapy for the treatment of psoriasis, with 56% receiving prior conventional systemic therapy and 43% receiving prior biologic therapy. A total of 28% of subjects had a history of psoriatic arthritis.

In both trials, the endpoints were the proportion of subjects who achieved at least a 75% reduction in PASI score (PASI 75) from baseline to Week 12 and treatment success (cleared or minimal) on the Physician's Global Assessment (PGA). The PGA is a 6-category scale ranging from 0 (cleared) to 5 (severe) that indicates the physician's overall assessment of psoriasis focusing on plaque thickness/induration, erythema, and scaling.

Clinical Response

The results of Ps STUDY 1 and Ps STUDY 2 are presented in Table 8 below.

Table 8: Clinical Outcomes at Week 12 in Adult Subjects with Plaque Psoriasis in Ps STUDY 1 and Ps STUDY 2
 | Ps STUDY 1 |  |  | Ps STUDY 2
 |  | STELARA |  |  | STELARA
 | Placebo | 45 mg | 90 mg | Placebo | 45 mg | 90 mg
Subjects randomized | 255 | 255 | 256 | 410 | 409 | 411
PASI 75 response | 8 (3%) | 171 (67%) | 170 (66%) | 15 (4%) | 273 (67%) | 311 (76%)
PGA of Cleared or Minimal | 10 (4%) | 151 (59%) | 156 (61%) | 18 (4%) | 277 (68%) | 300 (73%)

Examination of age, gender, and race subgroups did not identify differences in response to STELARA among these subgroups.

In subjects who weighed 100 kg or less, response rates were comparable with both the 45 mg and 90 mg doses; however, in subjects who weighed greater than 100 kg, higher response rates were seen with 90 mg dosing compared with 45 mg dosing (Table 9 below).

Table 9: Clinical Outcomes by Weight at Week 12 in Adult Subjects with Plaque Psoriasis in Ps STUDY 1 and Ps STUDY 2
 | Ps STUDY 1 |  |  | Ps STUDY 2
 |  | STELARA |  |  | STELARA
 | Placebo | 45 mg | 90 mg | Placebo | 45 mg | 90 mg
Subjects randomized | 255 | 255 | 256 | 410 | 409 | 411
PASI 75 response [Subjects were dosed with trial medication at Weeks 0 and 4.]
≤100 kg | 4% | 74% | 65% | 4% | 73% | 78%
 | 6/166 | 124/168 | 107/164 | 12/290 | 218/297 | 225/289
>100 kg | 2% | 54% | 68% | 3% | 49% | 71%
 | 2/89 | 47/87 | 63/92 | 3/120 | 55/112 | 86/121
PGA of Cleared or Minimal
≤100 kg | 4% | 64% | 63% | 5% | 74% | 75%
 | 7/166 | 108/168 | 103/164 | 14/290 | 220/297 | 216/289
>100 kg | 3% | 49% | 58% | 3% | 51% | 69%
 | 3/89 | 43/87 | 53/92 | 4/120 | 57/112 | 84/121

Subjects in Ps STUDY 1 who were PASI 75 responders at both Weeks 28 and 40 were re-randomized at Week 40 to either continued dosing of STELARA (STELARA at Week 40) or to withdrawal of therapy (placebo at Week 40). At Week 52, 89% (144/162) of subjects re-randomized to STELARA treatment were PASI 75 responders compared with 63% (100/159) of subjects re-randomized to placebo (treatment withdrawal after Week 28 dose). The median time to loss of PASI 75 response among the subjects randomized to treatment withdrawal was 16 weeks.

14.2 Pediatric Subjects with Plaque Psoriasis

A multicenter, randomized, double blind, placebo-controlled trial (Ps STUDY 3) enrolled 110 pediatric subjects 12 years of age and older with a minimum BSA involvement of 10%, a PASI score greater than or equal to 12, and a PGA score greater than or equal to 3, who were candidates for phototherapy or systemic therapy and whose disease was inadequately controlled by topical therapy.

Subjects were randomized to receive placebo (n = 37), the recommended dose of STELARA (n = 36), or one-half the recommended dose of STELARA (n = 37) by subcutaneous injection at Weeks 0 and 4 followed by dosing every 12 weeks (q12w). The recommended dose of STELARA was 0.75 mg/kg for subjects weighing less than 60 kg, 45 mg for subjects weighing 60 kg to 100 kg, and 90 mg for subjects weighing greater than 100 kg. At Week 12, subjects who received placebo were crossed over to receive STELARA at the recommended dose or one-half the recommended dose.

Of the pediatric subjects, approximately 63% had prior exposure to phototherapy or conventional systemic therapy and approximately 11% had prior exposure to biologics.

The endpoints were the proportion of subjects who achieved a PGA score of cleared (0) or minimal (1), PASI 75, and PASI 90 at Week 12. Subjects were followed for up to 60 weeks following first administration of trial agent.

Clinical Response

The efficacy results at Week 12 for Ps STUDY 3 are presented in Table 10.

Table 10: Efficacy Results at Week 12 in Pediatric Subjects 12 Years of Age and Older with Plaque Psoriasis in Ps STUDY 3
 | Ps STUDY 3
 | Placebo n (%) | STELARA [Using the weight-based dosage regimen specified in Table 1 and Table 2.] n (%)
N | 37 | 36
PGA
PGA of cleared (0) or minimal (1) | 2 (5.4%) | 25 (69.4%)
PASI
PASI 75 responders | 4 (10.8%) | 29 (80.6%)
PASI 90 responders | 2 (5.4%) | 22 (61.1%)

14.3 Psoriatic Arthritis

The safety and efficacy of STELARA was assessed in 927 subjects (PsA STUDY 1, n=615; PsA STUDY 2, n=312), in two randomized, double-blind, placebo-controlled trials in adult subjects 18 years of age and older with active PsA (≥5 swollen joints and ≥5 tender joints) despite nonsteroidal anti-inflammatory (NSAID) or disease modifying antirheumatic (DMARD) therapy. Subjects in these trials had a diagnosis of PsA for at least 6 months. Subjects with each subtype of PsA were enrolled, including polyarticular arthritis with the absence of rheumatoid nodules (39%), spondylitis with peripheral arthritis (28%), asymmetric peripheral arthritis (21%), distal interphalangeal involvement (12%) and arthritis mutilans (0.5%). Over 70% and 40% of the patients, respectively, had enthesitis and dactylitis at baseline.

Subjects were randomized to receive treatment with STELARA 45 mg, 90 mg, or placebo subcutaneously at Weeks 0 and 4 followed by every 12 weeks (q12w) dosing. Approximately 50% of subjects continued on stable doses of MTX (≤25 mg/week). The primary endpoint was the percentage of subjects achieving ACR 20 response at Week 24.

In PsA STUDY 1 and PsA STUDY 2, 80% and 86% of the subjects, respectively, had been previously treated with DMARDs. In PsA STUDY 1, previous treatment with anti-tumor necrosis factor (TNF)-α agent was not allowed. In PsA STUDY 2, 58% (n=180) of the subjects had been previously treated with TNF blocker, of whom over 70% had discontinued their TNF blocker treatment for lack of efficacy or intolerance at any time.

Clinical Response

In both trials, a greater proportion of subjects achieved ACR 20, ACR 50 and PASI 75 response in the STELARA 45 mg and 90 mg groups compared to placebo at Week 24 (see Table 11). ACR 70 responses were also higher in the STELARA 45 mg and 90 mg groups, although the difference was only numerical (p=NS) in STUDY 2. Responses were consistent in subjects treated with STELARA alone or in combination with methotrexate. Responses were similar in subjects regardless of prior TNFα exposure.

Table 11: ACR 20, ACR 50, ACR 70 and PASI 75 Responses In PsA STUDY 1 And PsA STUDY 2 At Week 24
 | PsA STUDY 1 |  |  | PsA STUDY 2
 |  | STELARA |  |  | STELARA
 | Placebo | 45 mg | 90 mg | Placebo | 45 mg | 90 mg
Number of subjects randomized | 206 | 205 | 204 | 104 | 103 | 105
ACR 20 response, N (%) | 47 (23%) | 87 (42%) | 101 (50%) | 21 (20%) | 45 (44%) | 46 (44%)
ACR 50 response, N (%) | 18 (9%) | 51 (25%) | 57 (28%) | 7 (7%) | 18 (17%) | 24 (23%)
ACR 70 response, N (%) | 5 (2%) | 25 (12%) | 29 (14%) | 3 (3%) | 7 (7%) | 9 (9%)
Number of subjects with ≥ 3% BSA [Number of subjects with ≥ 3% BSA psoriasis skin involvement at baseline] | 146 | 145 | 149 | 80 | 80 | 81
PASI 75 response, N (%) | 16 (11%) | 83 (57%) | 93 (62%) | 4 (5%) | 41 (51%) | 45 (56%)

The percent of subjects achieving ACR 20 responses by visit is shown in Figure 1.

Figure 1: Percent of subjects achieving ACR 20 response through Week 24

PsA STUDY 1

The results of the components of the ACR response criteria are shown in Table 12.

Table 12: Mean Change From Baseline In ACR Components At Week 24
 | PsA STUDY 1
 |  | STELARA
 | Placebo (N = 206) | 45 mg (N = 205) | 90 mg (N = 204)
Number of swollen joints [Number of swollen joints counted (0–66)]
Baseline | 15 | 12 | 13
Mean Change at Week 24 | -3 | -5 | -6
Number of tender joints [Number of tender joints counted (0–68)]
Baseline | 25 | 22 | 23
Mean Change at Week 24 | -4 | -8 | -9
Subject's assessment of pain [Visual analogue scale; 0= best, 10=worst.]
Baseline | 6.1 | 6.2 | 6.6
Mean Change at Week 24 | -0.5 | -2.0 | -2.6
Subject global assessment
Baseline | 6.1 | 6.3 | 6.4
Mean Change at Week 24 | -0.5 | -2.0 | -2.5
Physician global assessment
Baseline | 5.8 | 5.7 | 6.1
Mean Change at Week 24 | -1.4 | -2.6 | -3.1
Disability index (HAQ) [Disability Index of the Health Assessment Questionnaire; 0 = best, 3 = worst, measures the patient's ability to perform the following: dress/groom, arise, eat, walk, reach, grip, maintain hygiene, and maintain daily activity.]
Baseline | 1.2 | 1.2 | 1.2
Mean Change at Week 24 | -0.1 | -0.3 | -0.4
CRP (mg/dL) [CRP: (Normal Range 0.0–1.0 mg/dL)]
Baseline | 1.6 | 1.7 | 1.8
Mean Change at Week 24 | 0.01 | -0.5 | -0.8

An improvement in enthesitis and dactylitis scores was observed in each STELARA group compared with placebo at Week 24.

Physical Function

STELARA-treated subjects showed improvement in physical function compared to subjects receiving placebo as assessed by HAQ-DI at Week 24. In both trials, the proportion of HAQ-DI responders (≥0.3 improvement in HAQ-DI score) was greater in the STELARA 45 mg and 90 mg groups compared to placebo at Week 24.

14.4 Crohn's Disease

STELARA was evaluated in three randomized, double-blind, placebo-controlled clinical trials in adult subjects with moderately to severely active Crohn's disease (Crohn's Disease Activity Index [CDAI] score of 220 to 450). There were two 8-week intravenous induction trials(CD-1 and CD-2) followed by a 44-week subcutaneous randomized withdrawal maintenance trial (CD-3) representing 52 weeks of therapy. Subjects in CD-1 had failed or were intolerant to treatment with one or more TNF blockers, while subjects in CD-2 had failed or were intolerant to treatment with immunomodulators or corticosteroids, but never failed treatment with a TNF blocker.

Trials CD-1 and CD-2

In trials CD-1 and CD-2, 1409 subjects were randomized, of whom 1368 (CD-1, n=741; CD-2, n=627) were included in the final efficacy analysis. Induction of clinical response (defined as a reduction in CDAI score of greater than or equal to 100 points or CDAI score of less than 150) at Week 6 and clinical remission (defined as a CDAI score of less than 150) at Week 8 were evaluated. In both trials, subjects were randomized to receive a single intravenous administration of STELARA at either approximately 6 mg/kg, placebo (see Table 4), or 130 mg (a lower dose than recommended).

In trial CD-1, subjects had failed or were intolerant to prior treatment with a TNF blocker: 29% subjects had an inadequate initial response (primary non-responders), 69% responded but subsequently lost response (secondary non-responders) and 36% were intolerant to a TNF blocker. Of these subjects, 48% failed or were intolerant to one TNF blocker and 52% had failed 2 or 3 prior TNF blockers. At baseline and throughout the trial, approximately 46% of the subjects were receiving corticosteroids and 31% of the subjects were receiving immunomodulators (AZA, 6-MP, MTX). The median baseline CDAI score was 319 in the STELARA approximately 6 mg/kg group and 313 in the placebo group.

In trial CD-2, subjects had failed or were intolerant to prior treatment with corticosteroids (81% of subjects), at least one immunomodulator (6-MP, AZA, MTX; 68% of subjects), or both (49% of subjects). Additionally, 69% never received a TNF blocker and 31% previously received but had not failed a TNF blocker. At baseline, and throughout the trial, approximately 39% of the subjects were receiving corticosteroids and 35% of the subjects were receiving immunomodulators (AZA, 6-MP, MTX). The median baseline CDAI score was 286 in the STELARA and 290 in the placebo group.

In these induction trials, a greater proportion of subjects treated with STELARA (at the recommended dose of approximately 6 mg/kg dose) achieved clinical response at Week 6 and clinical remission at Week 8 compared to placebo (see Table 13for clinical response and remission rates). Clinical response and remission were significant as early as Week 3 in STELARA-treated subjects and continued to improve through Week 8.

Table 13: Induction of Clinical Response and Remission in CD-1 [Patient population consisted of subjects who failed or were intolerant to TNF blocker therapy] and CD-2 [Patient population consisted of subjects who failed or were intolerant to corticosteroids or immunomodulators (e.g., 6-MP, AZA, MTX) and previously received but not failed a TNF blocker or were never treated with a TNF blocker.]
 | CD-1 n = 741 |  |  | CD-2 n = 627
 | Placebo N = 247 | STELARA [Infusion dose of STELARA using the weight-based dosage regimen specified in Table 4.] N = 249 | Treatment difference and 95% CI | Placebo N = 209 | STELARA N = 209 | Treatment difference and 95% CI
Clinical Response (100 point), Week 6 | 53 (21%) | 84 (34%) [0.001≤ p < 0.01] | 12% (4%, 20%) | 60 (29%) | 116 (56%) [p < 0.001] | 27% (18%, 36%)
Clinical Remission, Week 8 | 18 (7%) | 52 (21%) | 14% (8%, 20%) | 41 (20%) | 84 (40%) | 21% (12%, 29%)
Clinical Response (100 point), Week 8 | 50 (20%) | 94 (38%) | 18% (10%, 25%) | 67 (32%) | 121 (58%) | 26% (17%, 35%)
70 Point Response, Week 6 | 75 (30%) | 109 (44%) | 13% (5%, 22%) | 81 (39%) | 135 (65%) | 26% (17%, 35%)
70 Point Response, Week 3 | 67 (27%) | 101 (41%) | 13% (5%, 22%) | 66 (32%) | 106 (51%) | 19% (10%, 28%)
Clinical remission is defined as CDAI score < 150; Clinical response is defined as reduction in CDAI score by at least 100 points or being in clinical remission: 70 point response is defined as reduction in CDAI score by at least 70 points

Trial CD-3

The maintenance trial (CD-3), evaluated 388 subjects who achieved clinical response (≥100 point reduction in CDAI score) at Week 8 with either induction dose of STELARA in trials CD-1 or CD-2. Subjects were randomized to receive a subcutaneous maintenance regimen of either 90 mg STELARA every 8 weeks or placebo for 44 weeks (see Table 14).

Table 14: Clinical Response and Remission In CD-3 (Week 44; 52 Weeks From Initiation Of Induction Dose)
 | Placebo [The placebo group consisted of subjects who were in response to STELARA and were randomized to receive placebo at the start of maintenance therapy.] | 90 mg STELARA every 8 weeks | Treatment difference and 95% CI
 | N = 131 [Subjects who achieved clinical response to STELARA at the end of the induction trial.] | N = 128 | Treatment difference and 95% CI
Clinical Remission | 47 (36%) | 68 (53%) [p < 0.01] | 17% (5%, 29%)
Clinical Response | 58 (44%) | 76 (59%) [0.01≤ p < 0.05] | 15% (3%, 27%)
Clinical Remission in patients in remission at the start of maintenance therapy [Subjects in remission at the end of maintenance therapy who were in remission at the start of maintenance therapy. This does not account for any other time point during maintenance therapy.] | 36/79 (46%) | 52/78 (67%) | 21% (6%, 36%)
Clinical remission is defined as CDAI score < 150; Clinical response is defined as reduction in CDAI of at least 100 points or being in clinical remission

At Week 44, 47% of subjects who received STELARA were corticosteroid-free and in clinical remission, compared to 30% of subjects in the placebo group.

At Week 0 of trial CD-3, 34/56 (61%) STELARA-treated subjects who previously failed or were intolerant to TNF blocker therapies were in clinical remission and 23/56 (41%) of these subjects were in clinical remission at Week 44. In the placebo arm, 27/61 (44%) subjects were in clinical remission at Week 0 while 16/61 (26%) of these subjects were in remission at Week 44.

At Week 0 of trial CD-3, 46/72 (64%) STELARA-treated subjects who had previously failed immunomodulator therapy or corticosteroids (but not TNF blockers) were in clinical remission and 45/72 (63%) of these subjects were in clinical remission at Week 44. In the placebo arm, 50/70 (71%) of these subjects were in clinical remission at Week 0 while 31/70 (44%) were in remission at Week 44. In the subset of these subjects who were also naïve to TNF blockers, 34/52 (65%) of STELARA-treated subjects were in clinical remission at Week 44 as compared to 25/51 (49%) in the placebo arm.

Subjects who were not in clinical response 8 weeks after STELARA induction were not included in the primary efficacy analyses for trial CD-3; however, these subjects were eligible to receive a 90 mg subcutaneous injection of STELARA upon entry into trial CD-3. Of these subjects, 102/219 (47%) achieved clinical response eight weeks later and were followed for the duration of the trial.

14.5 Ulcerative Colitis

STELARA was evaluated in two randomized, double-blind, placebo-controlled clinical trials [UC-1 and UC-2 (NCT02407236)] in adult subjects with moderately to severely active ulcerative colitis who had an inadequate response to or failed to tolerate a biologic (i.e., TNF blocker and/or vedolizumab), corticosteroids, and/or 6-MP or AZA therapy. The 8-week intravenous induction trial (UC-1) was followed by the 44-week subcutaneous randomized withdrawal maintenance trial (UC-2) for a total of 52 weeks of therapy.

Disease assessment was based on the Mayo score, which ranged from 0 to 12 and has four subscores that were each scored from 0 (normal) to 3 (most severe): stool frequency, rectal bleeding, findings on centrally-reviewed endoscopy, and physician global assessment. Moderately to severely active ulcerative colitis was defined at baseline (Week 0) as Mayo score of 6 to 12, including a Mayo endoscopy subscore ≥2. An endoscopy score of 2 was defined by marked erythema, absent vascular pattern, friability, erosions; and a score of 3 was defined by spontaneous bleeding, ulceration. At baseline, subjects had a median Mayo score of 9, with 84% of subjects having moderate disease (Mayo score 6–10) and 15% having severe disease (Mayo score 11–12).

Subjects in these trials may have received other concomitant therapies including aminosalicylates, immunomodulatory agents (AZA, 6-MP, or MTX), and oral corticosteroids (prednisone).

Trial UC-1

In UC-1, 961 subjects were randomized at Week 0 to a single intravenous administration of STELARA of approximately 6 mg/kg, 130 mg (a lower dose than recommended), or placebo. Subjects enrolled in UC-1 had to have failed therapy with corticosteroids, immunomodulators or at least one biologic. A total of 51% had failed at least one biologic and 17% had failed both a TNF blocker and an integrin receptor blocker. Of the total population, 46% had failed corticosteroids or immunomodulators but were biologic-naïve and an additional 3% had previously received but had not failed a biologic. At induction baseline and throughout the trial, approximately 52% subjects were receiving oral corticosteroids, 28% subjects were receiving immunomodulators (AZA, 6-MP, or MTX) and 69% subjects were receiving aminosalicylates.

The primary endpoint was clinical remission at Week 8. Clinical remission with a definition of: Mayo stool frequency subscore of 0 or 1, Mayo rectal bleeding subscore of 0 (no rectal bleeding), and Mayo endoscopy subscore of 0 or 1 (Mayo endoscopy subscore of 0 defined as normal or inactive disease and Mayo subscore of 1 defined as presence of erythema, decreased vascular pattern and no friability) is provided in Table 15.

The secondary endpoints were clinical response, endoscopic improvement, and histologic-endoscopic mucosal improvement. Clinical response with a definition of (≥ 2 points and ≥ 30% decrease in modified Mayo score, defined as 3-component Mayo score without the Physician's Global Assessment, with either a decrease from baseline in the rectal bleeding subscore ≥1 or a rectal bleeding subscore of 0 or 1), endoscopic improvement with a definition of Mayo endoscopy subscore of 0 or 1, and histologic-endoscopic mucosal improvement with a definition of combined endoscopic improvement and histologic improvement of the colon tissue [neutrophil infiltration in <5% of crypts, no crypt destruction, and no erosions, ulcerations, or granulation tissue] are provided in Table 15.

In UC-1, a significantly greater proportion of subjects treated with STELARA (at the recommended dose of approximately 6 mg/kg dose) were in clinical remission and response and achieved endoscopic improvement and histologic-endoscopic mucosal improvement compared to placebo (see Table 15).

Table 15: Proportion of Subjects Meeting Efficacy Endpoints at Week 8 in UC-1
Endpoint | Placebo N = 319 |  | STELARA [Infusion dose of STELARA using the weight-based dosage regimen specified in Table 4.] N = 322 |  | Treatment difference and 97.5% CI [Adjusted treatment difference (97.5% CI)]
Endpoint | N | % | N | % | Treatment difference and 97.5% CI [Adjusted treatment difference (97.5% CI)]
Clinical Remission [Clinical remission was defined as Mayo stool frequency subscore of 0 or 1, Mayo rectal bleeding subscore of 0, and Mayo endoscopy subscore of 0 or 1 (modified so that 1 does not include friability).] | 22 | 7% | 62 | 19% | 12% (7%, 18%) [p < 0.001]
Bio-naïve [An additional 7 subjects on placebo and 9 subjects on STELARA (6 mg/kg) had been exposed to, but had not failed, biologics.] | 14/151 | 9% | 36/147 | 24%
Prior biologic failure | 7/161 | 4% | 24/166 | 14%
Endoscopic Improvement [Endoscopic improvement was defined as Mayo endoscopy subscore of 0 or 1 (modified so that 1 does not include friability).] | 40 | 13% | 80 | 25% | 12% (6%, 19%)
Bio-naïve | 28/151 | 19% | 43/147 | 29%
Prior biologic failure | 11/161 | 7% | 34/166 | 20%
Clinical Response [Clinical response was defined as a decrease from baseline in the modified Mayo score by ≥30% and ≥2 points, with either a decrease from baseline in the rectal bleeding subscore ≥1 or a rectal bleeding subscore of 0 or 1.] | 99 | 31% | 186 | 58% | 27% (18%, 35%)
Bio-naïve | 55/151 | 36% | 94/147 | 64%
Prior biologic failure | 42/161 | 26% | 86/166 | 52%
Histologic-Endoscopic Mucosal Improvement [Histologic-endoscopic mucosal improvement was defined as combined endoscopic improvement (Mayo endoscopy subscore of 0 or 1) and histologic improvement of the colon tissue (neutrophil infiltration in <5% of crypts, no crypt destruction, and no erosions, ulcerations, or granulation tissue).] | 26 | 8% | 54 | 17% | 9% (3%, 14%)
Bio-naïve | 19/151 | 13% | 30/147 | 20%
Prior biologic failure | 6/161 | 4% | 21/166 | 13%

The relationship of histologic-endoscopic mucosal improvement, as defined in UC-1, at Week 8 to disease progression and long-term outcomes was not evaluated during UC-1.

Rectal Bleeding and Stool Frequency Subscores

Decreases in rectal bleeding and stool frequency subscores were observed as early as Week 2 in STELARA-treated subjects.

Trial UC-2

The maintenance trial (UC-2) evaluated 523 subjects who achieved clinical response 8 weeks following the intravenous administration of either induction dose of STELARA in UC-1. These subjects were randomized to receive a subcutaneous maintenance regimen of either 90 mg STELARA every 8 weeks, or every 12 weeks (a lower dose than recommended), or placebo for 44 weeks.

The primary endpoint was the proportion of subjects in clinical remission at Week 44. The secondary endpoints included the proportion of subjects maintaining clinical response at Week 44, the proportion of subjects with endoscopic improvement at Week 44, the proportion of subjects with corticosteroid-free clinical remission at Week 44, and the proportion of subjects maintaining clinical remission at Week 44 among subjects who achieved clinical remission 8 weeks after induction.

Results of the primary and secondary endpoints at Week 44 in subjects treated with STELARA at the recommended dosage (90 mg every 8 weeks) compared to the placebo are shown in Table 16.

Table 16: Efficacy Endpoints of Maintenance at Week 44 in UC-2 (52 Weeks from Initiation of the Induction Dose)
Endpoint | Placebo [The placebo group consisted of subjects who were in response to STELARA and were randomized to receive placebo at the start of maintenance therapy.] N = 175 [Clinical response was defined as a decrease from baseline in the modified Mayo score by ≥30% and ≥2 points, with either a decrease from baseline in the rectal bleeding subscore ≥1 or a rectal bleeding subscore of 0 or 1.] |  | 90 mg STELARA every 8 weeks N = 176 |  | Treatment difference and 95% CI
Endpoint | N | % | N | % | Treatment difference and 95% CI
Clinical Remission [Clinical remission was defined as Mayo stool frequency subscore of 0 or 1, Mayo rectal bleeding subscore of 0, and Mayo endoscopy subscore of 0 or 1 (modified so that 1 does not include friability).] | 46 | 26% | 79 | 45% | 19% (9%, 28%) [p =<0.001]
Bio-naïve [An additional 3 subjects on placebo and 6 subjects on STELARA had been exposed to, but had not failed, biologics.] | 30/84 | 36% | 39/79 | 49%
Prior biologic failure | 16/88 | 18% | 37/91 | 41%
Maintenance of Clinical Response at Week 44 | 84 | 48% | 130 | 74% | 26% (16%, 36%)
Bio-naïve | 49/84 | 58% | 62/79 | 78%
Prior biologic failure | 35/88 | 40% | 64/91 | 70%
Endoscopic Improvement [Endoscopic improvement was defined as Mayo endoscopy subscore of 0 or 1 (modified so that 1 does not include friability).] | 47 | 27% | 83 | 47% | 20% (11%, 30%)
Bio-naïve | 29/84 | 35% | 42/79 | 53%
Prior biologic failure | 18/88 | 20% | 38/91 | 42%
Corticosteroid-free Clinical Remission [Corticosteroid-free clinical remission was defined as subjects in clinical remission and not receiving corticosteroids at Week 44.] | 45 | 26% | 76 | 43% | 17% (8%, 27%)
Bio-naïve | 30/84 | 36% | 38/79 | 48%
Prior biologic failure | 15/88 | 17% | 35/91 | 38%
Maintenance of Clinical Remission at Week 44 in subjects who achieved clinical remission 8 weeks after induction | 18/50 | 36% | 27/41 | 66% | 31% (12%, 50%) [p=0.004]
Bio-naïve | 12/27 | 44% | 14/20 | 70%
Prior biologic failure | 6/23 | 26% | 12/18 | 67%

Other Endpoints

Week 16 Responders to Ustekinumab Induction

Subjects who were not in clinical response 8 weeks after induction with STELARA in UC-1 were not included in the primary efficacy analyses for trial UC-2; however, these subjects were eligible to receive a 90 mg subcutaneous injection of STELARA at Week 8. Of these subjects, 55/101 (54%) achieved clinical response eight weeks later (Week 16) and received STELARA 90 mg subcutaneously every 8 weeks during the UC-2 trial. At Week 44, there were 97/157 (62%) subjects who maintained clinical response and there were 51/157 (32%) who achieved clinical remission.

Histologic-Endoscopic Mucosal Improvement at Week 44

The proportion of subjects achieving histologic-endoscopic mucosal improvement during maintenance treatment in UC-2 was 75/172 (44%) among subjects on STELARA and 40/172 (23%) in subjects on placebo at Week 44. The relationship of histologic-endoscopic mucosal improvement, as defined in UC-2, at Week 44 to progression of disease or long-term outcomes was not evaluated in UC-2.

Endoscopic Normalization

Normalization of endoscopic appearance of the mucosa was defined as a Mayo endoscopic subscore of 0. At Week 8 in UC-1, endoscopic normalization was achieved in 25/322 (8%) of subjects treated with STELARA and 12/319 (4%) of subjects in the placebo group. At Week 44 of UC-2, endoscopic normalization was achieved in 51/176 (29%) of subjects treated with STELARA and in 32/175 (18%) of subjects in placebo group.

15 REFERENCES

^1 Surveillance, Epidemiology, and End Results (SEER) Program (www.seer.cancer.gov) SEER*Stat Database: Incidence - SEER 6.6.2 Regs Research Data, Nov 2009 Sub (1973–2007) - Linked To County Attributes - Total U.S., 1969–2007 Counties, National Cancer Institute, DCCPS, Surveillance Research Program, Surveillance Systems Branch, released April 2010, based on the November 2009 submission.

16 HOW SUPPLIED/STORAGE AND HANDLING

STELARA®(ustekinumab) injection is a sterile, preservative-free, colorless to light yellow solution and may contain a few small translucent or white particles. It is supplied as individually packaged, single-dose prefilled syringes or single-dose vials.

For Subcutaneous Use

Prefilled Syringes

- 45 mg/0.5 mL (NDC 57894-060-03)
- 90 mg/mL (NDC 57894-061-03)

Each prefilled syringe is equipped with a 27 -gauge fixed ½ inch needle, a needle safety guard, and a needle cover that contains dry natural rubber.

Single-dose Vial

- 45 mg/0.5 mL (NDC 57894-060-02)

For Intravenous Infusion

Single-dose Vial

- 130 mg/26 mL (5 mg/mL) (NDC 57894-054-27)

Storage and Stability

Store STELARA vials and prefilled syringes refrigerated between 2 °C to 8 °C (36 °F to 46 °F). Store STELARA vials upright. Keep the product in the original carton to protect from light until the time of use. Do not freeze. Do not shake.

If needed, individual prefilled syringes may be stored at room temperature up to 30 °C (86 °F) for a maximum single period of up to 30 days in the original carton to protect from light. Record the date when the prefilled syringe is first removed from the refrigerator on the carton in the space provided. Once a syringe has been stored at room temperature, do not return to the refrigerator. Discard the syringe if not used within 30 days at room temperature storage. Do not use STELARA after the expiration date on the carton or on the prefilled syringe.

17 PATIENT COUNSELING INFORMATION

Advise the patient and/or caregiver to read the FDA-approved patient labeling (Medication Guide and Instructions for Use).

Infections

Inform patients that STELARA may lower the ability of their immune system to fight infections and to contact their healthcare provider immediately if they develop any signs or symptoms of infection [see Warnings and Precautions (5.1)] .

Malignancies

Inform patients of the risk of developing malignancies while receiving STELARA [see Warnings and Precautions (5.4)] .

Serious Hypersensitivity and Reactions

- Inform patients that serious hypersensitivity reactions have been reported with intravenous and subcutaneous administration of STELARA. Instruct patients to discontinue STELARA and seek immediate medical attention if they experience any signs or symptoms of hypersensitivity reactions [see Warnings and Precautions (5.5)].
- Inform patients the needle cover on the prefilled syringe contains dry natural rubber (a derivative of latex), which may cause allergic reactions in individuals sensitive to latex [see Dosage and Administration (2.4)].

Posterior Reversible Encephalopathy Syndrome (PRES)

Inform patients to immediately contact their healthcare provider if they experience signs and symptoms of PRES (which may include headache, seizures, confusion, or visual disturbances) [see Warnings and Precautions (5.6)] .

Immunizations

Inform patients that STELARA can interfere with the usual response to immunizations and that they should avoid live vaccines [see Warnings and Precautions (5.7)] .

Administration

Instruct patients to follow sharps disposal recommendations, as described in the Instructions for Use.

Prefilled Syringe Manufactured by: Janssen Biotech, Inc., Horsham, PA 19044, USA. U.S. License No. 1864 at Baxter Pharmaceutical Solutions, Bloomington, IN 47403 and at Cilag AG, Schaffhausen, Switzerland

Vial Manufactured by: Janssen Biotech, Inc., Horsham, PA 19044, USA. U.S. License No. 1864 at Cilag AG, Schaffhausen, Switzerland

For patent information: www.janssenpatents.com

© Johnson & Johnson and its affiliates 2025

MEDICATION GUIDE
STELARA®(stel ar a)
(ustekinumab)
injection, for subcutaneous or intravenous use

What is the most important information I should know about STELARA?
STELARA is a medicine that affects your immune system. STELARA can increase your risk of having serious side effects, including:

- Serious infections.STELARA may lower the ability of your immune system to fight infections and may increase your risk of infections. Some people have serious infections during treatment with STELARA, including tuberculosis (TB), and infections caused by bacteria, fungi, or viruses. Some people have to be hospitalized for treatment of their infection.
  - Your healthcare provider should check you for TB before starting STELARA.
  - If your healthcare provider feels that you are at risk for TB, you may be treated with medicine for TB before you begin treatment with STELARA and during treatment with STELARA.
  - Your healthcare provider should watch you closely for signs and symptoms of TB while you are being treated with STELARA.

You should not start STELARA if you have any kind of infection unless your healthcare provider says it is okay.

Before starting STELARA, tell your healthcare provider if you:

- think you have an infection or have symptoms of an infection such as:

- fever, sweat, or chills
- muscle aches
- cough
- shortness of breath
- blood in phlegm

- weight loss
- warm, red, or painful skin or sores on your body
- diarrhea or stomach pain
- burning when you urinate or urinate more often than normal
- feel very tired

- are being treated for an infection or have any open cuts.
- get a lot of infections or have infections that keep coming back.
- have TB or have been in close contact with someone with TB.

After starting STELARA, call your healthcare provider right away if you have any symptoms of an infection (see above). These may be signs of infections such as chest infections, or skin infections or shingles that could have serious complications. STELARA can make you more likely to get infections or make an infection that you have worse.

- People who havea genetic problem where the body does not make any of the proteins interleukin 12 (IL-12) and interleukin 23 (IL-23) are at a higher risk for certain serious infections. These infections can spread throughout the body and cause death. People who take STELARA may also be more likely to get these infections.
- Cancers.STELARA may decrease the activity of your immune system and increase your risk for certain types of cancers. Tell your healthcare provider if you have ever had any type of cancer. Some people who are receiving STELARA and have risk factors for skin cancer have developed certain types of skin cancers. During your treatment with STELARA, tell your healthcare provider if you develop any new skin growths.

What is STELARA?
STELARA is a prescription medicine used to treat:

- adults and children 6 years of age and older with moderate to severe plaque psoriasis who may benefit from taking injections or pills (systemic therapy) or phototherapy (treatment using ultraviolet light alone or with pills).
- adults and children 6 years of age and older with active psoriatic arthritis.
- adults with moderately to severely active Crohn's disease.
- adults with moderately to severely active ulcerative colitis.

It is not known if STELARA is safe and effective in children with Crohn’s disease or ulcerative colitis or in children less than 6 years of age with plaque psoriasis or psoriatic arthritis.

Who should not use STELARA?
Do not use STELARA if you areallergic to ustekinumab or any of the ingredients in STELARA. See the end of this Medication Guide for a complete list of ingredients in STELARA.

Before you use or receive STELARA, tell your healthcare provider about all of your medical conditions, including if you:

- have any of the conditions or symptoms listed in the section " What is the most important information I should know about STELARA?"
- ever had an allergic reaction to STELARA. Ask your healthcare provider if you are not sure.
- are allergic to latex. The needle cover on the prefilled syringe contains latex.
- have recently received or are scheduled to receive an immunization (vaccine). People who are being treated with STELARA should avoid receiving live vaccines. Tell your healthcare provider if anyone in your house needs a live vaccine. The viruses used in some types of live vaccines can spread to people with a weakened immune system, and can cause serious problems. You should avoid receiving the BCG vaccine during the one year before receiving STELARA or one year after you stop receiving STELARA.
- have any new or changing lesions within psoriasis areas or on normal skin.
- are receiving or have received allergy shots, especially for serious allergic reactions. Allergy shots may not work as well for you during treatment with STELARA. STELARA may also increase your risk of having an allergic reaction to an allergy shot.
- receive or have received phototherapy for your psoriasis.
- are pregnant or plan to become pregnant. It is not known if STELARA can harm your unborn baby. You and your healthcare provider should decide if you will receive STELARA.
- are breastfeeding or plan to breastfeed. STELARA can pass into your breast milk.
- Talk to your healthcare provider about the best way to feed your baby if you receive STELARA.

Tell your healthcare provider about all the medicines you take, including prescription and over-the-counter medicines, vitamins, and herbal supplements.

Know the medicines you take. Keep a list of them to show your healthcare provider and pharmacist when you get a new medicine.

How should I use STELARA?

- Use STELARA exactly as the healthcare provider tells you to. The healthcare provider will determine the right dose of STELARA, the amount for each injection, and how often it should be given. Be sure to keep all scheduled follow-up appointments.
- The needle cover on the STELARA prefilled syringe contains latex. Do not handle the needle cover if you are sensitive to latex.
- Adults with Crohn's disease and ulcerative colitis will receive the first dose of STELARA through a vein in the arm (intravenous infusion) in a healthcare facility by a healthcare provider. It takes at least 1 hour to receive the full dose of medicine. STELARA will then be received as an injection under the skin (subcutaneous injection) 8 weeks after the first dose of STELARA, as described below.
- Adults and children 6 years of age and older with plaque psoriasis or psoriatic arthritis will receive STELARA as an injection under the skin as described below.
- Injecting STELARA under the skin
  - STELARA is intended for use under the guidance and supervision of a healthcare provider.
  - In children, it is recommended that STELARA be administered by a healthcare provider. If ahealthcare provider decides that you or a caregiver may give the injections of STELARA at home, you or a caregiver should receive training on the right way to prepare and inject STELARA.
  - Do not try to inject STELARA until you have been shown how to inject STELARA by a healthcare provider.
  - STELARA can be injected under the skin in the upper arms, buttocks, upper legs (thighs) or stomach area (abdomen).
  - Do not give an injection in an area of the skin that is tender, bruised, red or hard.
  - Use a different injection site each time you use STELARA.
- If you inject too much STELARA, call the healthcare provider or Poison Help line at 1-800-222-1222, or go to the nearest emergency room right away.

Read the detailed Instructions for Use at the end of this Medication Guide for instructions about how to prepare and inject a dose of STELARA, and how to properly throw away (dispose of) used needles, syringes, and vials. The syringe, needle, and vial must never be re-used. After the rubber stopper is punctured, STELARA can become contaminated by harmful bacteria which could cause an infection if re-used. Therefore, throw away any unused portion of STELARA.

What should I avoid while using STELARA?

You should avoid receiving a live vaccine during treatment with STELARA. See " Before you use or receive STELARA, tell your healthcare provider about all of your medical conditions, including if you:"

What are the possible side effects of STELARA?
STELARA may cause serious side effects, including:

- See " What is the most important information I should know about STELARA?"
- Serious allergic reactions.Serious allergic reactions including death can occur with STELARA. Stop using STELARA and get medical help right away if you get any of the following symptoms of a serious allergic reaction:

- feeling faint
- swelling of your face, eyelids, tongue, or throat
- chest discomfort

- trouble breathing
- skin rash

- Posterior Reversible Encephalopathy Syndrome (PRES).PRES is a rare condition that affects the brain and can cause death. Tell your healthcare provider right away if you get any symptoms of PRES during treatment with STELARA, including:

- headache
- seizures

- confusion
- vision problems

- Lung inflammation.Cases of lung inflammation have happened in some people who receive STELARA, and may be serious. These lung problems may need to be treated in a hospital. Tell your healthcare provider right away if you develop shortness of breath or a cough that doesn't go away during treatment with STELARA .

The most common side effects of STELARA include:

- nasal congestion, sore throat, and runny nose
- upper respiratory infections
- fever
- headache
- tiredness
- itching
- nausea and vomiting
- influenza

- redness at the injection site
- vaginal yeast infections
- urinary tract infections
- sinus infection
- bronchitis
- diarrhea
- stomach pain
- joint pain

These are not all of the possible side effects of STELARA. Call your doctor for medical advice about side effects. You may report side effects to FDA at 1-800-FDA-1088.
You may also report side effects to Janssen Biotech, Inc. at 1-800-526-7736.

How should I store STELARA?

- Store STELARA vials and prefilled syringes in a refrigerator between 36 °F to 46 °F (2 °C to 8 °C).
- Store STELARA vials standing up straight (upright).
- Store STELARA in the original carton to protect it from light until time to use it.
- Do not freeze STELARA.
- Do not shake STELARA.
- If needed, individual STELARA prefilled syringes may also be stored at room temperature up to 86 °F (30 °C) for a maximum single period of up to 30 days in the original carton to protect from light.
- Record the date when the prefilled syringe is first removed from the refrigerator on the carton in the space provided.
- After a prefilled syringe has been stored at room temperature, do not return it to the refrigerator.
- Throw away (discard) the prefilled syringe if it is not used within 30 days at room temperature storage.
- Do not use STELARA after the expiration date on the carton or on the prefilled syringe.

Keep STELARA and all medicines out of the reach of children.

General information about the safe and effective use of STELARA.
Medicines are sometimes prescribed for purposes other than those listed in a Medication Guide. Do not use STELARA for a condition for which it was not prescribed. Do not give STELARA to other people, even if they have the same symptoms that you have. It may harm them. You can ask your pharmacist or healthcare provider for information about STELARA that was written for health professionals.

What are the ingredients in STELARA?
Active ingredient: ustekinumab
Inactive ingredients: Single-dose prefilled syringe and single-dose vial for subcutaneous usecontain L-histidine, L-histidine monohydrochloride monohydrate, Polysorbate 80, and sucrose. Single-dose vial for intravenous infusioncontains EDTA disodium salt dihydrate, L-histidine, L-histidine hydrochloride monohydrate, L-methionine, Polysorbate 80, and sucrose.
Manufactured by: Janssen Biotech, Inc., Horsham, PA 19044, USA. U.S. License No. 1864
© Johnson & Johnson and its affiliates 2025.
For more information, go to www.stelarainfo.comor call 1-800-526-7736.

This Medication Guide has been approved by the U.S. Food and Drug Administration.

Revised:11/2025

INSTRUCTIONS FOR USE
STELARA (stel ar a)
(ustekinumab)
injection, for subcutaneous use

This Instructions for Use contains information on how to inject STELARA using a prefilled syringe.

Read this Instructions for Use before you start using STELARA. A healthcare provider should show you how to prepare and give an injection of STELARA the right way.

If you cannot give the injection:

- ask your healthcare provider to help you, or
- ask someone who has been trained by a healthcare provider to give your injections.

Do not try to inject STELARA until you have been shown how to inject STELARA by a healthcare provider.

Important information You Need to Know Before Injecting STELARA:

- For subcutaneous use only(inject directly under the skin).
- Before you start, check the carton to make sure that it is the right dose. You will have either 45 mg or 90 mg as prescribed by the healthcare provider.
  - If the dose is 45 mg, you will receive one 45 mg prefilled syringe.
  - If the dose is 90 mg, you will receive either one 90 mg prefilled syringe or two 45 mg prefilled syringes. If you receive two 45 mg prefilled syringes for a 90 mg dose, you will need to give two injections, one right after the other.
- Check the expiration date on the prefilled syringe and carton. If the expiration date has passed or if the prefilled syringe has been kept at room temperature up to 86°F (30°C) for longer than a maximum single period of 30 days or if the prefilled syringe has been stored above 86°F (30°C), do not use it. If the expiration date has passed or if the prefilled syringe has been stored above 86°F (30°C) or at room temperature for longer than 30 days, call the healthcare provider or pharmacist, or call 1-800-526-7736 for help.
- Make sure the syringe is not damaged.
- The needle cover on the prefilled syringe contains latex. Do not handle the needle cover on the STELARA prefilled syringe if you are allergic to latex.
- Check the prefilled syringe for any particles or discoloration. The liquid in the prefilled syringe should look clear and colorless to light yellow with a few small clear or white particles.
- Do not use if it is frozen, discolored, cloudy or has large particles. Get a new prefilled syringe.
- Do not shake the prefilled syringe at any time. Shaking the prefilled syringe may damage the STELARA medicine. If the prefilled syringe has been shaken, do not use it. Get a new prefilled syringe.
- To reduce the risk of accidental needle sticks, each prefilled syringe has a needle guard that is automatically activated to cover the needle after you have given the injection. Do not pull back on the plunger at any time.

Storing STELARA prefilled syringes

- Store STELARA prefilled syringes in the refrigerator between 36°F to 46°F (2°C to 8°C).
- Store STELARA prefilled syringes in the original carton to protect from light.
- Do not freeze STELARA prefilled syringes.
- If needed, STELARA prefilled syringe may be stored at room temperature up to 86°F (30°C) for a maximum single period of up to 30 days in the original carton to protect from light.
- Record the date when the prefilled syringe is removed from the refrigerator on the carton in the space provided.
- After a prefilled syringe has been stored at room temperature, do not return it to the refrigerator.
- Throw away (discard) the prefilled syringe if it is not used within 30 days at room temperature storage.

Keep STELARA and all medicines out of the reach of children.

Gather the supplies you will need to prepare and to give the injection. (See Figure A)

You will need:

- antiseptic wipes
- cotton balls or gauze pads
- adhesive bandage
- your prescribed dose of STELARA (See Figure B)
- FDA-cleared sharps disposal container. See " Step 4: Disposing of the syringes"

Figure A

Figure B

To prevent early activation of the needle safety guard, do not touch the NEEDLE GUARD ACTIVATION CLIPS at any time during use.

Step 1: Preparing the injection

- Choose a well-lit, clean, flat work surface.
- Wash your hands well with soap and warm water.
- Hold the prefilled syringe with the covered needle pointing upward.

Step 2: Preparing the injection site

- Choose an injection site around the stomach area (abdomen), buttocks, upper legs (thighs). If a caregiver is giving the injection, the outer area of the upper arms may also be used. (See Figure C)
- Use a different injection site for each injection. Do not give an injection in an area of the skin that is tender, bruised, red or hard.
- Clean the skin with an antiseptic wipe where you plan to give the injection.
- Do not touch this area again before giving the injection. Let the skin dry before injecting.
- Do not fan or blow on the clean area.

Figure C

*Areas in gray are recommended injection sites.

Step 3: Injecting STELARA

- Remove the needle cover when you are ready to inject STELARA.
- Do not touch the plunger or plunger head while removing the needle cover.
- Hold the body of the prefilled syringe with one hand and pull the needle cover straight off. (see Figure D)
- Put the needle cover in the trash.
- You may also see a drop of liquid at the end of the needle. This is normal.
- Do not touch the needle or let it touch anything.
- Do not use the prefilled syringe if it is dropped without the needle cover in place.

Figure D

- Hold the body of the prefilled syringe in one hand between the thumb and index fingers. (See Figure E)

Figure E

- Do not pull back on the plunger at any time.
- Use the other hand to gently pinch the cleaned area of skin. Hold firmly.
- Use a quick, dart-like motion to insert the needle into the pinched skin at about a 45-degree angle. (See Figure F)

Figure F

- Inject all of the liquid by using your thumb to push in the plunger until the plunger head is completely between the needle guard wings. (See Figure G)

Figure G

- When the plunger is pushed as far as it will go, keep pressure on the plunger head. Take the needle out of the skin and then let go of the skin.
- Slowly take your thumb off the plunger head. This will let the empty syringe move up until the entire needle is covered by the needle guard. (See Figure H)

Figure H

- When the needle is pulled out of the skin, there may be a little bleeding at the injection site. This is normal. You can press a cotton ball or gauze pad to the injection site if needed. Do not rub the injection site. You may cover the injection site with a small adhesive bandage, if necessary.

If the dose is 90 mg, you will receive either one 90 mg prefilled syringe or two 45 mg prefilled syringes. If you receive two 45 mg prefilled syringes for a 90 mg dose, you will need to give a second injection right after the first. Repeat Steps 1 to 3 for the second injection using a new syringe. Choose a different site for the second injection.

Step 4: Disposing of the syringes.

- Put the syringe in a FDA-cleared sharps disposal container right away after use. Do not throw away (dispose of) syringes in your household trash.
- If you do not have a FDA-cleared sharps disposal container, you may use a household container that is:
  - made of heavy-duty plastic
  - can be closed with a tight-fitting, puncture-resistant lid, without sharps being able to come out.
  - upright and stable during use,
  - leak-resistant,
  - and properly labeled to warn of hazardous waste inside the container.
- When your sharps disposal container is almost full, you will need to follow your community guidelines for the right way to dispose of your sharps disposal container. There may be local or state laws about how to throw away syringes and needles. For more information about safe sharps disposal, and for specific information about sharps disposal in the state that you live in, go to the FDA's website at: http://www.fda.gov/safesharpsdisposal.
- Do not dispose of your sharps disposal container in your household trash unless your community guidelines permit this. Do not recycle your sharps disposal container.
- If you have any questions, talk to your healthcare provider or pharmacist.

Prefilled Syringe Manufactured by:
Janssen Biotech, Inc., Horsham, PA 19044, USA License No. 1864 at Baxter Pharmaceutical Solutions, Bloomington, IN 47403 and at Cilag AG, Schaffhausen, Switzerland

This Instructions for Use has been approved by the U.S. Food and Drug Administration.

Revised: 06/2025

© Johnson & Johnson and its affiliates 2025

INSTRUCTIONS FOR USE
STELARA (stel ar a)
(ustekinumab)
injection, for subcutaneous use

This Instructions for Use contains information on how to inject STELARA using a vial.

Read this Instructions for Use before you start using STELARA. A healthcare provider should show you how to prepare, measure the dose, and give an injection of STELARA the right way.

If you cannot give the injection:

- ask your healthcare provider to help you, or
- ask someone who has been trained by a healthcare provider to give the injections.

Do not try to inject STELARA until you have been shown how to inject STELARA by a healthcare provider.

Important information You Need to Know Before Injecting STELARA:

- Before you start, check the carton to make sure that it is the right dose. You will have either 45 mg or 90 mg as prescribed by the healthcare provider.
  - If the dose is 45 mg or less you will receive one 45 mg vial.
  - If the dose is 90 mg, you will receive two 45 mg vials and you will need to give two injections, one right after the other.
- Check the expiration date on the vial and carton. If the expiration date has passed, do not use it. If the expiration date has passed, call the healthcare provider or pharmacist, or call 1-800-526-7736 for help.
- Check the vial for any particles or discoloration. The liquid in the vial should look clear and colorless to light yellow with a few small clear or white particles.
- Do not use if it is frozen, discolored, cloudy or has large particles. Get a new vial.
- Do not shake the vial at any time.Shaking the vial may damage the STELARA medicine. If the vial has been shaken, do not use it. Get a new vial.
- Do not use a STELARA vial more than one time, even if there is medicine left in the vial. After the rubber stopper is punctured, STELARA can become contaminated by harmful bacteria which could cause an infection if re-used. Therefore, throw away any unused STELARA after you give the injection.
- Safely throw away (dispose of) STELARA vials, needles, and syringes after use. See " Step 6: Disposing of needles, syringes, and vials."
- Do not re-use syringes or needles.
- To avoid needle-stick injuries, do notrecap needles.

Storing STELARA vials

- Store STELARA vials in a refrigerator between 36°F to 46°F (2°C to 8°C).
- Store STELARA vials standing up straight (upright).
- Store STELARA vials in the original carton to protect from light until the time of use.
- Do notfreeze STELARA vials.

Keep STELARA and all medicines out of the reach of children.

Gather the supplies you will need to prepare STELARA and to give your injection. (See Figure A)

You will need:

- a syringe with the needle attached, you will need a prescription from a healthcare provider to get syringes with the needles attached from a pharmacy.
- antiseptic wipes
- cotton balls or gauze pads
- adhesive bandage
- your prescribed dose of STELARA
- FDA-cleared sharps disposal container. See " Step 6: Disposing of needles, syringes, and vials."

Figure A

Step 1: Preparing the injection.

- Choose a well-lit, clean, flat work surface.
- Wash your hands well with soap and warm water.

Step 2: Preparing your injection site

- Choose an injection site around your stomach area (abdomen), buttocks, and upper legs (thighs).
- If a caregiver is giving you the injection, the outer area of the upper arms may also be used. (See Figure B)
- Use a different injection site for each injection. Do notgive an injection in an area of the skin that is tender, bruised, red or hard.
- Clean the skin with an antiseptic wipe where you plan to give the injection.
- Do nottouch this area again before giving the injection. Let the skin dry before injecting.
- Do notfan or blow on the clean area.

Figure B

*Areas in gray are recommended injection sites.

Step 3: Preparing the vial

- Remove the cap from the top of the vial. Throw away the cap but do not remove the rubber stopper. (See Figure C)

Figure C

- Clean the rubber stopper with an antiseptic wipe. (See Figure D)

Figure D

- Do not touch the rubber stopper after you clean it.
- Put the vial on a flat surface.

Step 4: Preparing the syringe

- Pick up the syringe with the needle attached.
- Remove the cap that covers the needle. (See Figure E)
- Throw the needle cap away. Do not touch the needle or allow the needle to touch anything.

Figure E

- Carefully pull back on the plunger to the line that matches the dose prescribed by the healthcare provider.
- Hold the vial between your thumb and index (pointer) finger.
- Use your other hand to push the syringe needle through the center of the rubber stopper. (See Figure F)

Figure F

- Push down on the plunger until all of the air has gone from the syringe into the vial.
- Turn the vial and the syringe upside down. (See Figure G)
- Hold the STELARA vial with one hand.
- It is important that the needle is always in the liquid in order to prevent air bubbles forming in the syringe.
- Pull back on the syringe plunger with your other hand.
- Fill the syringe until the black tip of the plunger lines up with the mark that matches the prescribed dose.

Figure G

- Do not remove the needle from the vial.Hold the syringe with the needle pointing up to see if it has any air bubbles inside.
- If there are air bubbles, gently tap the side of the syringe until the air bubbles rise to the top. (See Figure H)
- Slowly press the plunger up until all of the air bubbles are out of the syringe (but none of the liquid is out).
- Remove the syringe from the vial. Do not lay the syringe down or allow the needle to touch anything.

Figure H

Step 5: Injecting STELARA

- Hold the barrel of the syringe in one hand, between the thumb and index fingers.
- Do notpull back on the plunger at any time.
- Use the other hand to gently pinch the cleaned area of skin. Hold firmly.
- Use a quick, dart-like motion to insert the needle into the pinched skin at about a 45-degree angle. (See Figure I)

Figure I

- Push the plunger with your thumb as far as it will go to inject all of the liquid. Push it slowly and evenly, keeping the skin gently pinched.
- When the syringe is empty, pull the needle out of the skin and then let go of the skin. (See Figure J)

Figure J

- When the needle is pulled out of the skin, there may be a little bleeding at the injection site. This is normal. You can press a cotton ball or gauze pad to the injection site if needed. Do not rub the injection site. You may cover the injection site with a small adhesive bandage, if necessary.

If the dose is 90 mg, you will receive two 45 mg vials and you will need to give a second injection right after the first. Repeat Steps 1 to 5 using a new syringe.Choose a different site for the second injection.

Step 6: Disposing of the needles, syringes, and vials.

- Do notre-use a syringe or needle.
- To avoid needle-stick injuries, do not recap a needle.
- Put the needles and syringes in an FDA-cleared sharps disposal container right away after use. Do not throw away (dispose of) needles and syringes in your household trash.
- If you do not have an FDA-cleared sharps disposal container, you may use a household container that is:
  - made of heavy-duty plastic,
  - can be closed with a tight-fitting, puncture-resistant lid, without sharps being able to come out,
  - upright and stable during use,
  - leak-resistant,
  - and properly labeled to warn of hazardous waste inside the container.
- When your sharps disposal container is almost full, you will need to follow your community guidelines for the right way to dispose of your sharps disposal container. There may be local or state laws about how to throw away syringes and needles. For more information about safe sharps disposal, and for specific information about sharps disposal in the state that you live in, go to the FDA's website at: http://www.fda.gov/safesharpsdisposal.
- Do not dispose of your sharps disposal container in your household trash unless your community guidelines permit this. Do not recycle your sharps disposal container.
- Throw away the vial into the container where you put the syringes and needles.
- If you have any questions, talk to your healthcare provider or pharmacist.

Vial Manufactured by: Janssen Biotech, Inc., Horsham, PA 19044, USA License No. 1864 at Cilag AG, Schaffhausen, Switzerland

This Instructions for Use has been approved by the U.S. Food and Drug Administration.
Revised: 06/2025

© Johnson & Johnson and its affiliates 2025

PRINCIPAL DISPLAY PANEL - 45 mg/0.5 mL Vial Carton

NDC 57894-060-02

Single-dose vial.
Discard unused portion.

Stelara®
(ustekinumab)
Injection

45 mg/0.5 mL

For Subcutaneous Use

Attention: Dispense the enclosed
Medication Guide to each patient.

Rx only

Each vial contains 0.5 mL

Johnson
& Johnson

PRINCIPAL DISPLAY PANEL - 45 mg/0.5 mL Syringe Carton

Stelara®
(ustekinumab)
Injection

45 mg/0.5 mL

For subcutaneous use

Contains one 45 mg/0.5 mL syringe

NDC 57894-060-03

Single-dose prefilled syringe - Discard unused portion

The 45 mg prefilled syringe contains:
45 mg ustekinumab, 0.5 mg L-histidine and L-histidine
monohydrochloride monohydrate, 0.02 mg polysorbate 80,
and 38 mg sucrose to fill a final volume of 0.5 mL

See package insert for dosing information

Rx only

ATTENTION: Dispense the enclosed Medication Guide
to each patient.

© 2009 Janssen

PRINCIPAL DISPLAY PANEL - 90 mg/mL Syringe Carton

Stelara®
(ustekinumab)
Injection

90 mg/mL

For subcutaneous use

Contains one 90 mg/mL syringe

NDC 57894-061-03

Single-dose prefilled syringe - Discard unused portion

The 90 mg prefilled syringe contains:
90 mg ustekinumab, 1 mg L-histidine and L-histidine
monohydrochloride monohydrate, 0.04 mg polysorbate 80,
and 76 mg sucrose to fill a final volume of 1 mL

See package insert for dosing information

Rx only

ATTENTION: Dispense the enclosed Medication
Guide to each patient.

© 2009 Janssen

PRINCIPAL DISPLAY PANEL - 130 mg/26 mL Vial Carton

NDC 57894-054-27

Single-Dose vial
Discard unused portion

Stelara®
(ustekinumab)
Injection

130 mg/26 mL
(5 mg/mL)

For Intravenous Infusion Only
Must be diluted

ATTENTION: Dispense
the enclosed Medication
Guide to each patient.

Rx only

janssen